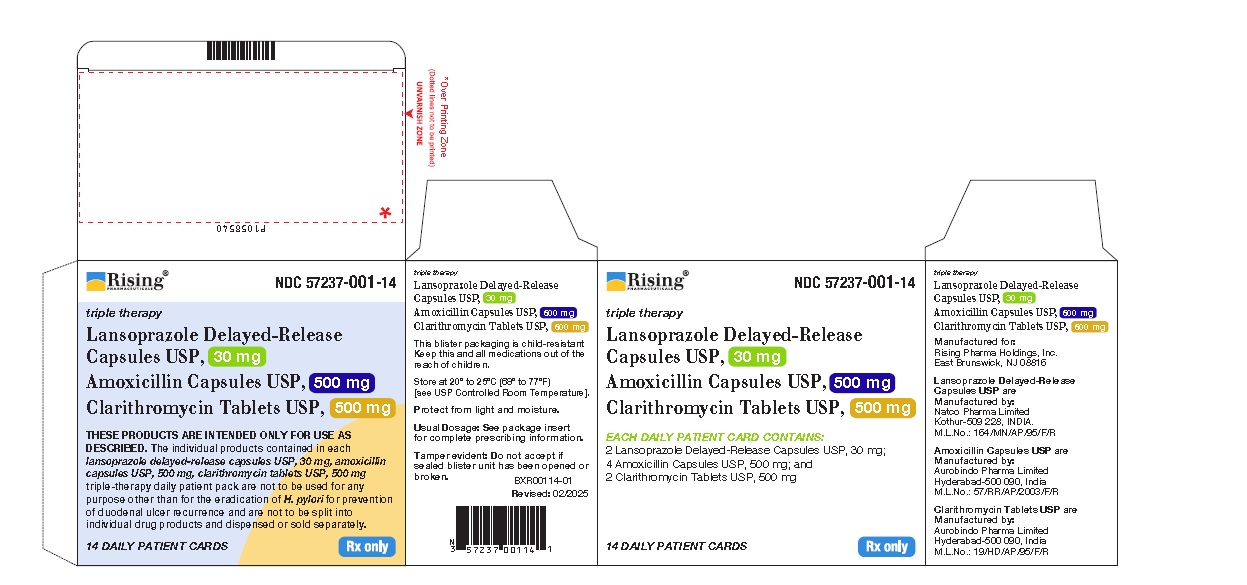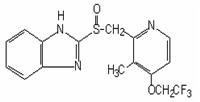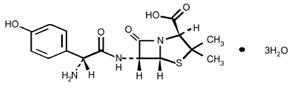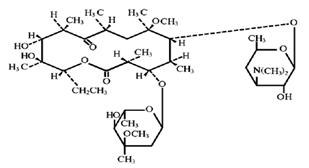 DRUG LABEL: Lansoprazole, Amoxicillin, Clarithromycin
NDC: 57237-001 | Form: KIT | Route: ORAL
Manufacturer: Rising Pharma Holdings, Inc.
Category: prescription | Type: Human Prescription Drug Label
Date: 20250219

ACTIVE INGREDIENTS: LANSOPRAZOLE 30 mg/1 1; AMOXICILLIN 500 mg/1 1; CLARITHROMYCIN 500 mg/1 1
INACTIVE INGREDIENTS: ACETONE; HYPROMELLOSE, UNSPECIFIED; ISOPROPYL ALCOHOL; MAGNESIUM CARBONATE; METHACRYLIC ACID AND ETHYL ACRYLATE COPOLYMER; POLYETHYLENE GLYCOL 4000; POLYSORBATE 80; STARCH, CORN; TALC; TITANIUM DIOXIDE; D&C RED NO. 28; FD&C BLUE NO. 1; FD&C RED NO. 40; GELATIN, UNSPECIFIED; SODIUM LAURYL SULFATE; D&C RED NO. 28; FD&C BLUE NO. 1; FD&C RED NO. 40; GELATIN, UNSPECIFIED; SODIUM LAURYL SULFATE; TITANIUM DIOXIDE; MAGNESIUM STEARATE; MICROCRYSTALLINE CELLULOSE; SILICON DIOXIDE; CROSCARMELLOSE SODIUM; HYDROXYPROPYL CELLULOSE, UNSPECIFIED; HYPROMELLOSE 2910 (15 MPA.S); FERRIC OXIDE YELLOW; MAGNESIUM STEARATE; MICROCRYSTALLINE CELLULOSE; POVIDONE K30; PROPYLENE GLYCOL; SORBIC ACID; TITANIUM DIOXIDE; VANILLIN

Lansoprazole Delayed-Release Capsules USP, 30 mg, Amoxicillin Capsules USP, 500 mg, and Clarithromycin Tablets USP, 500 mg
Rx only

To reduce the development of drug-resistant bacteria and maintain the effectiveness of lansoprazole delayed-release capsules, amoxicillin capsules, and clarithromycin tablets and other antibacterial drugs, lansoprazole delayed-release capsules, amoxicillin capsules, and clarithromycin tablets should be used only to treat or prevent infections that are proven or strongly suspected to be caused by bacteria.
THESE PRODUCTS ARE INTENDED ONLY FOR USE AS DESCRIBED. The individual products contained in this package should not be used alone or in combination for other purposes. The information described in this labeling concerns only the use of these products as indicated in this daily administration pack. For information on use of the individual components when dispensed as individual medications outside this combined use for treating Helicobacter pylori (H. pylori), please see the package inserts for each individual product.

DESCRIPTION

Lansoprazole delayed-release capsules USP, amoxicillin capsules USP, and clarithromycin tablets USP consist of a daily administration card containing two lansoprazole 30 mg delayed-release capsules USP, four amoxicillin 500 mg capsules USP, and two clarithromycin 500 mg tablets USP, for oral administration.
Lansoprazole Delayed-Release Capsules, USP
The active ingredient in lansoprazole delayed-release capsules USP is lansoprazole, a proton pump inhibitor. Its empirical formula is C16H14F3N3O2S with a molecular weight of 369.37. Lansoprazole has the following structure:

Lansoprazole USP is a white to brownish-white odorless crystalline powder which melts with decomposition at approximately 166°C. Lansoprazole is freely soluble in dimethylformamide; soluble in methanol; sparingly soluble in ethanol; slightly soluble in ethyl acetate, dichloromethane and acetonitrile; very slightly soluble in ether; and practically insoluble in hexane and water.

Each delayed-release capsule contains enteric-coated pellets consisting of 30 mg of lansoprazole USP (active ingredient) and the following inactive ingredients: acetone, hypromellose, isopropyl alcohol, light magnesium carbonate, methacrylic acid copolymer, polyethylene glycol, polysorbate 80, sugar spheres (which contain sucrose and corn starch), talc, and titanium dioxide. Components of the gelatin capsule include D&C Red No. 28, FD&C Blue No. 1, FD&C Red No. 40, gelatin, sodium lauryl sulfate, and titanium dioxide.

Amoxicillin Capsules, USP

Amoxicillin, is a penicillin class antibacterial, with a broad spectrum of bactericidal activity against many gram-positive and gram-negative microorganisms. Chemically it is (2S, 5R, 6R)-6-[(R)-(-)-2-amino-2-(p-hydroxyphenyl)acetamido]-3,3-dimethyl-7-oxo-4-thia-1-azabicyclo[3.2.0] heptane-2-carboxylic acid trihydrate. The molecular formula is C16H19N3O5S•3H2O and the molecular weight of 419.45. Amoxicillin has the following structure:

Amoxicillin capsules USP are intended for oral administration.

The pink body with blue cap capsules contain amoxicillin trihydrate equivalent to 500 mg of amoxicillin USP. Inactive ingredients: Capsule shells - D&C Red No. 28, FD&C Blue No. 1, FD&C Red No. 40, gelatin, sodium lauryl sulfate and titanium dioxide; Capsule contents – magnesium stearate, microcrystalline cellulose.

Meets USP Dissolution Test 2.
Clarithromycin Tablets, USP
Clarithromycin is a macrolide antimicrobial. Chemically, it is 6-O-methylerythromycin. The molecular formula is C38H69NO13, and the molecular weight is 747.96. Clarithromycin has the following structure:

Clarithromycin USP is a white or almost white, crystalline powder. It is soluble in acetone, slightly soluble in methanol, ethanol, and acetonitrile, and practically insoluble in water.

Each light yellow colored, oval shaped, biconvex film-coated immediate-release tablet contains 500 mg of clarithromycin USP and the following inactive ingredients: colloidal silicon dioxide, croscarmellose sodium, hydroxypropyl cellulose, hypromellose, iron oxide yellow, magnesium stearate, microcrystalline cellulose, povidone, propylene glycol, sorbic acid, titanium dioxide, and vanillin.

CLINICAL PHARMACOLOGY

Pharmacokinetics

Pharmacokinetics when all three components of the lansoprazole delayed-release capsules, amoxicillin capsules, and clarithromycin tablets were coadministered has not been studied. Studies have shown no clinically significant interactions of lansoprazole delayed-release capsules and amoxicillin or lansoprazole delayed-release capsules and clarithromycin when administered together. There is no information about the gastric mucosal concentrations of lansoprazole delayed-release capsules, amoxicillin and clarithromycin after administration of these agents concomitantly. The systemic pharmacokinetic information presented below is based on studies in which each product was administered alone.
Lansoprazole Delayed-Release Capsules
Absorption
Lansoprazole delayed-release capsules contain an enteric-coated granule formulation of lansoprazole (because lansoprazole is acid-labile), so that absorption of lansoprazole begins only after the granules leave the stomach. The mean peak plasma levels of lansoprazole occur at approximately 1.7 hours. After a single-dose administration of 15 to 60 mg of oral lansoprazole, the peak plasma concentrations (Cmax) of lansoprazole and the area under the plasma concentration curves (AUCs) of lansoprazole were approximately proportional to the administered dose. Lansoprazole does not accumulate and its pharmacokinetics are unaltered by multiple dosing. The absolute bioavailability is over 80%. In healthy subjects, the mean (±SD) plasma half-life was 1.5 (±1.0) hours. Both the Cmax and AUC are diminished by about 50 to 70% if lansoprazole is given 30 minutes after food, compared to the fasting condition. There is no significant food effect if lansoprazole is given before meals.
Distribution
Lansoprazole is 97% bound to plasma proteins. Plasma protein binding is constant over the concentration range of 0.05 to 5 mcg/mL.
Elimination
Metabolism
Lansoprazole is extensively metabolized in the liver. Two metabolites have been identified in measurable quantities in plasma (the hydroxylated sulfinyl and sulfone derivatives of lansoprazole). These metabolites have very little or no antisecretory activity. Lansoprazole is thought to be transformed into two active species which inhibit acid secretion by blocking the proton pump [(H^+,K^+)-ATPase enzyme system] at the secretory surface of the gastric parietal cell. The two active species are not present in the systemic circulation. The plasma elimination half-life of lansoprazole is less than two hours while the acid inhibitory effect lasts more than 24 hours. Therefore, the plasma elimination half-life of lansoprazole does not reflect its duration of suppression of gastric acid secretion.
Excretion
Following single-dose oral administration of lansoprazole delayed-release capsules, virtually no unchanged lansoprazole was excreted in the urine. In one study, after a single oral dose of ^14C-lansoprazole, approximately one-third of the administered radiation was excreted in the urine and two-thirds was recovered in the feces. This implies a significant biliary excretion of the lansoprazole metabolites.
Amoxicillin
Absorption
Amoxicillin is stable in the presence of gastric acid and may be given without regard to meals. It is rapidly absorbed after oral administration. Orally administered doses of 500 mg amoxicillin capsules result in average peak blood levels one to two hours after administration in the range of 5.5 mcg/mL to 7.5 mcg/mL.
Distribution
Amoxicillin diffuses readily into most body tissues and fluids, with the exception of brain and spinal fluid, except when meninges are inflamed. In blood serum, amoxicillin is approximately 20% protein-bound.
Metabolism/Elimination
The elimination half-life of amoxicillin is 61.3 minutes. Detectable serum levels are observed up to eight hours after an orally administered dose of amoxicillin. Approximately 60% of the orally administered dose of amoxicillin is excreted unchanged in the urine within six to eight hours post-dose; its excretion can be delayed by concurrent administration of probenecid.
Clarithromycin
Absorption
Clarithromycin is rapidly absorbed from the gastrointestinal tract after oral administration. The absolute bioavailability of 250 mg clarithromycin tablets was approximately 50%. For a single 500 mg dose of clarithromycin, food slightly delays the onset of clarithromycin absorption, increasing the peak time from approximately two to 2.5 hours. Food also increases the clarithromycin peak plasma concentration by about 24%, but does not affect the extent of clarithromycin bioavailability. Food does not affect the onset of formation of the antimicrobially active metabolite, 14-OH clarithromycin or its peak plasma concentration but does slightly decrease the extent of metabolite formation, indicated by an 11% decrease in area under the plasma concentration-time curve (AUC). Therefore, clarithromycin tablets may be given without regard to food.
In nonfasting, healthy human subjects (males and females), peak plasma concentrations were attained within two to three hours after oral dosing. Steady-state peak plasma clarithromycin concentrations were attained within three days and were approximately 3 to 4 mcg/mL with a 500 mg dose administered every eight to 12 hours.
Metabolism/Elimination
The elimination half-life of clarithromycin was five to seven hours with 500 mg administered every eight to 12 hours. The nonlinearity of clarithromycin pharmacokinetics is slight at the recommended dose of 500 mg administered every eight to 12 hours. With a 500 mg every eight to 12 hours dosing, the peak steady-state concentration of 14-OH clarithromycin is up to 1 mcg/mL, and its elimination half-life is about seven to nine hours. The steady-state concentration of this metabolite is generally attained within three to four days.
After a 500 mg tablet every 12 hours, the urinary excretion of clarithromycin is approximately 30%. The renal clearance of clarithromycin approximates the normal glomerular filtration rate. The major metabolite found in urine is 14-OH clarithromycin, which accounts for an additional 10% to 15% of the dose with a 500 mg tablet administered every 12 hours.
Steady-state concentrations of clarithromycin and 14-OH clarithromycin observed following administration of 500 mg doses of clarithromycin every 12 hours to adult patients with HIV infection were similar to those observed in healthy volunteers. In adult HIV-infected patients taking 500 mg doses of clarithromycin every 12 hours, steady-state clarithromycin Cmax values ranged from 2 to 4 mcg/mL.
The steady-state concentrations of clarithromycin in subjects with impaired hepatic function did not differ from those in normal subjects; however, the 14-OH clarithromycin concentrations were lower in the hepatically impaired subjects. The decreased formation of 14-OH clarithromycin was at least partially offset by an increase in renal clearance of clarithromycin in the subjects with impaired hepatic function when compared to healthy subjects.
The pharmacokinetics of clarithromycin was also altered in subjects with impaired renal function (see PRECAUTIONSand DOSAGE AND ADMINISTRATION).
Clarithromycin and the 14-OH clarithromycin metabolite distribute readily into body tissues and fluids. There are no data available on cerebrospinal fluid penetration. Because of high intercellular concentrations, tissue concentrations are higher than serum concentrations.

Special Populations

Geriatric Patients
The clearance of lansoprazole is decreased in the elderly; with elimination half-life increased approximately 50% to 100%. Because the mean half-life in the elderly remains between 1.9 to 2.9 hours, repeated once daily dosing does not result in accumulation of lansoprazole. Peak plasma levels were not increased in the elderly.
Male and Female Patients
In a study comparing 12 male and six female human subjects who received lansoprazole, no sex-related differences were found in pharmacokinetics and intragastric pH results.
Racial or Ethnic Groups
The pooled mean pharmacokinetic parameters of lansoprazole from twelve U.S. studies (N=513) were compared to the mean pharmacokinetic parameters from two Asian studies (N=20). The mean AUCs of lansoprazole in Asian subjects were approximately twice those seen in pooled U.S. data; however, the inter-individual variability was high. The Cmax values were comparable.
Patients with Renal Impairment
In patients with severe renal impairment, plasma protein binding decreased by 1 to 1.5% after administration of 60 mg of lansoprazole. Patients with renal impairment had a shortened elimination half-life and decreased total AUC (free and bound). The AUC for free lansoprazole in plasma, however, was not related to the degree of renal impairment; and the Cmax and Tmax (time to reach the maximum concentration) were not different than the Cmax and Tmax from subjects with normal renal function. Therefore, the pharmacokinetics of lansoprazole were not clinically different in patients with mild, moderate or severe renal impairment compared to healthy subjects with normal renal function.
Patients with Hepatic Impairment
In patients with mild (Child-Pugh Class A) or moderate (Child-Pugh Class B) hepatic impairment there was an approximate 3-fold increase in mean AUC compared to healthy subjects with normal hepatic function following multiple oral doses of 30 mg lansoprazole delayed-release capsules for 7 days. The corresponding mean plasma half-life of lansoprazole was prolonged from 1.5 hours to 4 hours (Child-Pugh A) or 5 hours (Child-Pugh B).
In patients with compensated and decompensated cirrhosis, there was an approximate 6- and 5-fold increase in AUC, respectively, compared to healthy subjects with normal hepatic function following a single oral dose of 30 mg lansoprazole (see DOSAGE AND ADMINISTRATION).

Drug Interaction Studies

Effect of Lansoprazole on Other Drugs

Cytochrome P450 Interactions

Lansoprazole is metabolized through the cytochrome P450 system, specifically through the CYP3A and CYP2C19 isozymes. Studies have shown that lansoprazole does not have clinically significant interactions with other drugs metabolized by the cytochrome P450 system, such as warfarin, antipyrine, indomethacin, ibuprofen, phenytoin, propranolol, prednisone, diazepam, or clarithromycin in healthy subjects. These compounds are metabolized through various cytochrome P450 isozymes including CYP1A2, CYP2C9, CYP2C19, CYP2D6, and CYP3A.

Theophylline

When lansoprazole was administered concomitantly with theophylline (CYP1A2, CYP3A), a minor increase (10%) in the clearance of theophylline was seen. Because of the small magnitude and the direction of the effect on theophylline clearance, this interaction is unlikely to be of clinical concern (see PRECAUTIONS, Drug Interactions).

Methotrexate and 7-hydroxymethotrexate

In an open-label, single-arm, eight day, pharmacokinetic study of 28 adult rheumatoid arthritis patients (who required the chronic use of 7.5 to 15 mg of methotrexate given weekly), administration of seven days of naproxen 500 mg twice daily and lansoprazole 30 mg daily had no effect on the pharmacokinetics of methotrexate and 7-hydroxymethotrexate. While this study was not designed to assess the safety of this combination of drugs, no major adverse reactions were noted. However, this study was conducted with low doses of methotrexate. A drug interaction study with high doses of methotrexate has not been conducted (see WARNINGS).

Amoxicillin

Lansoprazole has also been shown to have no clinically significant interaction with amoxicillin.

Sucralfate

In a single-dose crossover study examining lansoprazole 30 mg administered alone and concomitantly with sucralfate 1 gram, absorption of lansoprazole was delayed and the bioavailability was reduced by 17% when administered concomitantly with sucralfate (see PRECAUTIONS, Drug Interactions).

Antacids

In clinical trials, antacids were administered concomitantly with lansoprazole and there was no evidence of a change in the efficacy of lansoprazole.

Clopidogrel

Clopidogrel is metabolized to its active metabolite in part by CYP2C19. A study of healthy subjects who were CYP2C19 extensive metabolizers, receiving once daily administration of clopidogrel 75 mg alone or concomitantly with lansoprazole 30 mg (n=40), for nine days was conducted. The mean AUC of the active metabolite of clopidogrel was reduced by approximately 14% (mean AUC ratio was 86%, with 90% CI of 80 to 92%) when lansoprazole was coadministered compared to administration of clopidogrel alone.

Pharmacodynamic parameters were also measured and demonstrated that the change in inhibition of platelet aggregation (induced by 5 mcM ADP) was related to the change in the exposure to clopidogrel active metabolite. The effect on exposure to the active metabolite of clopidogrel and on clopidogrel-induced platelet inhibition is not considered clinically important.

Effect of Other Drugs on Lansoprazole

Because lansoprazole is metabolized by CYP2C19 and CYP3A4, inducers and inhibitors of these enzymes may potentially alter exposure of lansoprazole.

Pharmacodynamics

Microbiology
Lansoprazole, clarithromycin and/or amoxicillin have been shown to be active against most strains of Helicobacter pylori in vitro and in clinical infections as described in the INDICATIONS AND USAGE section.
Helicobacter pylori Pretreatment Resistance
Clarithromycin pretreatment resistance rates were 9.5% (91/960) by E-test and 11.3% (12/106) by agar dilution in the dual and triple therapy clinical trials (M93-125, M93-130, M93-131, M95-392, and M95-399).
Amoxicillin pretreatment susceptible isolates (≤0.25 mcg/mL) occurred in 97.8% (936/957) and 98% (98/100) of the patients in the dual and triple therapy clinical trials by E-test and agar dilution, respectively. Twenty-one of 957 patients (2.2%) by E-test, and two of 100 patients (2%) by agar dilution, had amoxicillin pretreatment MICs of greater than 0.25 mcg/mL. One patient on the 14-day triple therapy regimen had an unconfirmed pretreatment amoxicillin minimum inhibitory concentration (MIC) of greater than 256 mcg/mL by E-test and the patient was eradicated of H. pylori.

Table 1: Clarithromycin Susceptibility Test Results and Clinical/Bacteriological Outcomes*

Clarithromycin Pretreatment Results |  | Clarithromycin Post-treatment Results
 |  | H. pylori negative - eradicated | H. pylori positive - not eradicated Post-treatment susceptibility results
 |  | H. pylori negative - eradicated | S† | I† | R† | No MIC
Triple Therapy 14-Day (lansoprazole 30 mg twice daily/amoxicillin 1 g twice daily/clarithromycin 500 mg twice daily) (M95-399, M93-131, M95-392)
Susceptible† | 112 | 105 |  |  |  | 7
Intermediate† | 3 | 3
Resistant† | 17 | 6 |  |  | 7 | 4
Triple Therapy 10-Day (lansoprazole 30 mg twice daily/amoxicillin 1 g twice daily/clarithromycin 500 mg twice daily) (M95-399)
Susceptible† | 42 | 40 | 1 |  | 1
Intermediate†
Resistant† | 4 | 1 |  |  | 3

* Includes only patients with pretreatment clarithromycin susceptibility test results
† Breakpoints for antimicrobial susceptibility testing at the time of the studies were: Susceptible (S) MIC ≤0.25 mcg/mL, Intermediate (I) MIC 0.5 to 1.0 mcg/mL, Resistant (R) MIC ≥2 mcg/mL. For current performance standards for antimicrobial susceptibility testing, see section below title, Susceptibility Test for Helicobacter pylori.

Patients not eradicated of H. pylori following lansoprazole/amoxicillin/clarithromycin triple therapy will likely have clarithromycin resistant H. pylori isolates. Therefore, for those patients who fail therapy, clarithromycin susceptibility testing should be done if possible. Patients with clarithromycin resistant H. pylori should not be treated with lansoprazole/amoxicillin/clarithromycin triple therapy or other regimens which include clarithromycin as the sole antimicrobial agent.
Amoxicillin Susceptibility Test Results and Clinical/Bacteriological Outcomes
In the dual and triple therapy clinical trials, 82.6% (195/236) of the patients that had pretreatment amoxicillin susceptible MICs (≤0.25 mcg/mL) were eradicated of H. pylori. Of those with pretreatment amoxicillin MICs of greater than 0.25 mcg/mL, three of six had the H. pylori eradicated. A total of 30% (21/70) of the patients failed lansoprazole 30 mg three times daily per amoxicillin 1 g three times daily dual therapy and a total of 12.8% (22/172) of the patients failed the 10- and 14-day triple therapy regimens. Post-treatment susceptibility results were not obtained on 11 of the patients who failed therapy. Nine of the 11 patients with amoxicillin post-treatment MICs that failed the triple therapy regimen also had clarithromycin resistant H. pylori isolates.
Susceptibility Test for Helicobacter pylori
The reference methodology for susceptibility testing of H. pylori is agar dilution MICs. ^1One to three microliters of an inoculum equivalent to a No. 2 McFarland standard (1 x 10^7 - 1 x 10^8CFU/mL for H. pylori) are inoculated directly onto freshly prepared antimicrobial containing Mueller-Hinton agar plates with 5% aged defibrinated sheep blood (greater than two weeks old). The agar dilution plates are incubated at 35°C in a microaerobic environment produced by a gas generating system suitable for Campylobacter species. After three days of incubation, the MICs are recorded as the lowest concentration of antimicrobial agent required to inhibit growth of the organism. The clarithromycin and amoxicillin MIC values should be interpreted according to the following criteria:

Susceptibility Test Interpretive Criteria for H. pylori
Clarithromycin MIC (mcg/mL)* | Interpretation
≤0.25 | Susceptible (S)
0.5 | Intermediate (I)
≥1 | Resistant (R)

Susceptibility Test Interpretive Criteria for H. pylori
Amoxicillin MIC (mcg/mL)*,† | Interpretation
<0.25 | Susceptible (S)

* These are tentative breakpoints for the agar dilution methodology and they should not be used to interpret results obtained using alternative methods.
† There were not enough organisms with MICs greater than 0.25 mcg/mL to determine a resistance breakpoint.

Standardized susceptibility test procedures require the use of laboratory control bacteria to monitor and ensure the accuracy and precision of supplies and reagents in the assay, and the techniques of the individual performing the test. Standard clarithromycin or amoxicillin powder should provide the following MIC ranges.

Acceptable Quality Control Ranges | Antimicrobial Agent | MIC (mcg/mL)*
H.pylori ATCC 43504 | Clarithromycin | 0.015 to 0.12
H.pylori ATCC 43504 | Amoxicillin | 0.015 to 0.12

* These are quality control ranges for the agar dilution methodology and should not be used to control test results obtained using alternative methods.

Antisecretory activity
After oral administration, lansoprazole was shown to significantly decrease the basal acid output and significantly increase the mean gastric pH and percent of time the gastric pH was greater than three and greater than four. Lansoprazole also significantly reduced meal-stimulated gastric acid output and secretion volume, as well as pentagastrin-stimulated acid output. In patients with hypersecretion of acid, lansoprazole significantly reduced basal and pentagastrin-stimulated gastric acid secretion. Lansoprazole inhibited the normal increases in secretion volume, acidity and acid output induced by insulin.
The intragastric pH results of a five-day, pharmacodynamic, crossover study of 15 mg and 30 mg of once daily lansoprazole are presented in Table 2.

Table 2: Mean Antisecretory Effects After Single and Multiple Daily Lansoprazole Delayed-Release Capsules Dosing
 |  | Lansoprazole Delayed-Release Capsules
Parameter | Baseline Value | 15 mg |  | 30 mg
Parameter | Baseline Value | Day 1 | Day 5 | Day 1 | Day 5
Mean 24 Hour pH | 2.1 | 2.7* | 4* | 3.6† | 4.9†
Mean Nighttime Hour pH | 1.9 | 2.4 | 3* | 2.6 | 3.8†
% Time Gastric pH>3 | 18 | 33* | 59* | 51† | 72†
% Time Gastric pH>4 | 12 | 22* | 49* | 41† | 66†

NOTE: An intragastric pH of greater than 4 reflects a reduction in gastric acid by 99%.
* (p<0.05) versus baseline only.
† (p<0.05) versus baseline and lansoprazole 15 mg.

After the initial dose in this study, increased gastric pH was seen within one to two hours with 30 mg of lansoprazole and two to three hours with 15 mg of lansoprazole. After multiple daily dosing, increased gastric pH was seen within the first hour post-dosing with 30 mg of lansoprazole and within one to two hours post-dosing with 15 mg of lansoprazole.
Acid suppression may enhance the effect of antimicrobials in eradicating Helicobacter pylori (H. pylori). The percentage of time gastric pH was elevated above five and six was evaluated in a crossover study of lansoprazole delayed-release capsules given daily, twice daily and three times daily.

Table 3: Mean Antisecretory Effects After 5 Days of Twice Daily and Three Times Daily Dosing
 | Lansoprazole Delayed-Release Capsules
Parameter | 30 mg daily | 15 mg twice daily | 30 mg twice daily | 30 mg three times daily
% Time Gastric pH>5 | 43 | 47 | 59* | 77†
% Time Gastric pH>6 | 20 | 23 | 28 | 45†

* (p<0.05) versus lansoprazole delayed-release capsules 30 mg daily
† (p<0.05) versus lansoprazole delayed-release capsules 30 mg daily, 15 mg twice daily and 30 mg twice daily

The inhibition of gastric acid secretion as measured by intragastric pH gradually returned to normal over two to four days after multiple doses. There was no indication of rebound gastric acidity.
Enterochromaffin-like (ECL) Cell Effects
During lifetime exposure of rats with up to 150 mg/kg/day of lansoprazole dosed seven days per week, marked hypergastrinemia was observed followed by ECL cell proliferation and formation of carcinoid tumors, especially in female rats. Gastric biopsy specimens from the body of the stomach from approximately 150 patients treated continuously with lansoprazole for at least one year did not show evidence of ECL cell effects similar to those seen in rat studies. Longer term data are needed to rule out the possibility of an increased risk of the development of gastric tumors in patients receiving long-term therapy with lansoprazole (see PRECAUTIONS, Carcinogenesis, Mutagenesis, Impairment of Fertility).
Other Gastric Effects in Humans
Lansoprazole did not significantly affect mucosal blood flow in the fundus of the stomach. Due to the normal physiologic effect caused by the inhibition of gastric acid secretion, a decrease of about 17% in blood flow in the antrum, pylorus, and duodenal bulb was seen. Lansoprazole significantly slowed the gastric emptying of digestible solids. Lansoprazole increased serum pepsinogen levels and decreased pepsin activity under basal conditions and in response to meal stimulation or insulin injection. As with other agents that elevate intragastric pH, increases in gastric pH were associated with increases in nitrate-reducing bacteria and elevation of nitrite concentration in gastric juice in patients with gastric ulcer. No significant increase in nitrosamine concentrations was observed.
Serum Gastrin Effects
In over 2100 patients, median fasting serum gastrin levels increased 50 to 100% from baseline but remained within normal range after treatment with 15 to 60 mg of oral lansoprazole. These elevations reached a plateau within two months of therapy and returned to pretreatment levels within four weeks after discontinuation of therapy.
Increased gastrin causes enterochromaffin-like cell hyperplasia and increased serum CgA levels. The increased CgA levels may cause false positive results in diagnostic investigations for neuroendocrine tumors (see WARNINGS).
Endocrine Effects
Human studies for up to one year have not detected any clinically significant effects on the endocrine system. Hormones studied include testosterone, luteinizing hormone (LH), follicle stimulating hormone (FSH), sex hormone binding globulin (SHBG), dehydroepiandrosterone sulfate (DHEA-S), prolactin, cortisol, estradiol, insulin, aldosterone, parathormone, glucagon, thyroid stimulating hormone (TSH), triiodothyronine (T3), thyroxine (T4), and somatotropic hormone (STH). Lansoprazole in oral doses of 15 to 60 mg for up to one year had no clinically significant effect on sexual function. In addition, lansoprazole in oral doses of 15 to 60 mg for two to eight weeks had no clinically significant effect on thyroid function. In 24 month carcinogenicity studies in Sprague-Dawley rats with daily lansoprazole dosages up to 150 mg/kg, proliferative changes in the Leydig cells of the testes, including benign neoplasm, were increased compared to control rats.
Other Effects
No systemic effects of lansoprazole on the central nervous system, lymphoid, hematopoietic, renal, hepatic, cardiovascular, or respiratory systems have been found in humans. Among 56 patients who had extensive baseline eye evaluations, no visual toxicity was observed after lansoprazole treatment (up to 180 mg/day) for up to 58 months. After lifetime lansoprazole exposure in rats, focal pancreatic atrophy, diffuse lymphoid hyperplasia in the thymus, and spontaneous retinal atrophy were seen.

CLINICAL STUDIES

H. pylori Eradication to Reduce the Risk of Duodenal Ulcer Recurrence

Randomized, double-blind clinical studies performed in the U.S. in patients with H. pylori and duodenal ulcer disease (defined as an active ulcer or history of an ulcer within one year) evaluated the efficacy of lansoprazole delayed-release capsules, amoxicillin capsules, and clarithromycin tablets as triple 14-day therapy for the eradication of H. pylori. The triple therapy regimen (lansoprazole delayed-release capsules 30 mg twice daily/amoxicillin 1 g twice daily/clarithromycin 500 mg twice daily) produced statistically significantly higher eradication rates than lansoprazole delayed-release capsules plus amoxicillin, lansoprazole delayed-release capsules plus clarithromycin, and amoxicillin plus clarithromycin dual therapies.

H. pylori eradication was defined as two negative tests (culture and histology) at four to six weeks following the end of treatment.

Triple therapy was shown to be more effective than all possible dual therapy combinations. The combination of lansoprazole delayed-release capsules plus amoxicillin and clarithromycin as triple therapy was effective in eradicating H. pylori. Eradication of H. pylori has been shown to reduce the risk of duodenal ulcer recurrence.

A randomized, double-blind clinical study performed in the U.S. in patients with H. pylori and duodenal ulcer disease (defined as an active ulcer or history of an ulcer within one year) compared the efficacy of lansoprazole delayed-release capsules triple therapy for ten and 14 days. This study established that the 10-day triple therapy was equivalent to the 14-day triple therapy in eradicating H. pylori.

Table 4 H. pylori Eradication Rates – Triple Therapy (Lansoprazole Delayed-Release Capsules/Amoxicillin/Clarithromycin) Percent of Patients Cured [95% Confidence Interval] (Number of patients)
Study | Duration | Triple Therapy Evaluable Analysis* | Triple Therapy Intent-to-Treat Analysis†
M93-131 | 14 days | 92‡ [80 to 97.7] (N=48) | 86‡ [73.3 to 93.5] (N=55)
M95-392 | 14 days | 86§ [75.7 to 93.6] (N=66) | 83§ [72 to 90.8] (N=70)
M95-399¶ | 14 days | 85 [77 to 91] (N=113) | 82 [73.9 to 88.1] (N=126)
 | 10 days | 84 [76 to 89.8] (N=123) | 81 [73.9 to 87.6] (N=135)

* Based on evaluable patients with confirmed duodenal ulcer (active or within one year) and H. pylori infection at baseline defined as at least two of three positive endoscopic tests from CLOtest, histology and/or culture. Patients were included in the analysis if they completed the study. Additionally, if patients dropped out of the study due to an adverse event related to the study drug, they were included in the evaluable analysis as failures of therapy.
† Patients were included in the analysis if they had documented H. pylori infection at baseline as defined above and had a confirmed duodenal ulcer (active or within one year). All dropouts were included as failures of therapy.
‡ (p<0.05) versus lansoprazole delayed-release capsules/amoxicillin and lansoprazole delayed-release capsules/clarithromycin dual therapy
§ (p<0.05) versus clarithromycin/amoxicillin dual therapy
¶ The 95% confidence interval for the difference in eradication rates, 10-day minus 14-day is (-10.5, 8.1) in the evaluable analysis and (-9.7, 9.1) in the intent-to-treat analysis.

INDICATIONS AND USAGE

H. pylori Eradication to Reduce the Risk of Duodenal Ulcer Recurrence
The components in lansoprazole delayed-release capsules, amoxicillin capsules, and clarithromycin tablets are indicated for the treatment of patients with H. pylori infection and duodenal ulcer disease (active or one-year history of a duodenal ulcer) to eradicate H. pylori. Eradication of H. pylori has been shown to reduce the risk of duodenal ulcer recurrence (see CLINICAL STUDIESand DOSAGE AND ADMINISTRATION).
To reduce the development of drug-resistant bacteria and maintain the effectiveness of lansoprazole delayed-release capsules, amoxicillin capsules, and clarithromycin tablets and other antibacterial drugs, lansoprazole delayed-release capsules, amoxicillin capsules, and clarithromycin tablets should be used only to treat or prevent infections that are proven or strongly suspected to be caused by susceptible bacteria. When culture and susceptibility information are available, they should be considered in selecting or modifying antibacterial therapy. In the absence of such data, local epidemiology and susceptibility patterns may contribute to the empiric selection of therapy.

CONTRAINDICATIONS

Lansoprazole delayed-release capsules, amoxicillin capsules, and clarithromycin tablets are contraindicated in patients with known severe hypersensitivity to any component of the formulation of lansoprazole delayed-release capsules. Hypersensitivity reactions may include anaphylaxis, anaphylactic shock, angioedema, bronchospasm, acute interstitial nephritis, and urticaria (see ADVERSE REACTIONS). Proton Pump Inhibitors (PPIs), including lansoprazole delayed-release capsules, are contraindicated with rilpivirine-containing products (see CLINICAL PHARMACOLOGY, Drug Interaction Studies).
A history of severe hypersensitivity reactions (e.g., anaphylaxis or Stevens-Johnson syndrome) to amoxicillin or other beta-lactam antibiotics (e.g., penicillins and cephalosporins) is a contraindication.
Clarithromycin is contraindicated in patients with a known hypersensitivity to clarithromycin, erythromycin, or any of the macrolide antibiotics.
Clarithromycin is contraindicated in patients with a history of cholestatic jaundice/hepatic dysfunction associated with prior use of clarithromycin. Clarithromycin is contraindicated with concomitant use of lurasidone due to the risk of an increase in lurasidone exposure and the potential for serious adverse reactions [(see PRECAUTIONS, Drug Interactions) (7)].
Clarithromycin should not be given to patients with history of QT prolongation or ventricular cardiac arrhythmia, including torsades de pointes.
Concomitant administration of clarithromycin, a component of lansoprazole delayed-release capsules, amoxicillin capsules, and clarithromycin tablets, and any of the following drugs is contraindicated: cisapride, pimozide, astemizole, terfenadine, ergotamine or dihydroergotamine (see PRECAUTIONS, Drug Interactions). There have been post-marketing reports of drug interactions when clarithromycin and/or erythromycin are coadministered with cisapride, pimozide, astemizole, or terfenadine resulting in cardiac arrhythmias (QT prolongation, ventricular tachycardia, ventricular fibrillation, and torsades de pointes) most likely due to inhibition of metabolism of these drugs by erythromycin and clarithromycin. Fatalities have been reported.
Concomitant administration of clarithromycin and colchicine is contraindicated in patients with renal or hepatic impairment.
Clarithromycin should not be used concomitantly with HMG-CoA reductase inhibitors (statins) that are extensively metabolized by CYP3A4 (lovastatin or simvastatin), due to the increase risk of myopathy, including rhabdomyolysis (see WARNINGS).

WARNINGS

Acute Hypersensitivity Reactions
Serious and occasionally fatal hypersensitivity (anaphylactic) reactions have been reported in patients on penicillin therapy, including amoxicillin. Although anaphylaxis is more frequent following parenteral therapy, it has occurred in patients on oral penicillins. These reactions are more likely to occur in individuals with a history of penicillin hypersensitivity and/or a history of sensitivity to multiple allergens. There have been reports of individuals with a history of penicillin hypersensitivity who have experienced severe reactions when treated with cephalosporins. Before initiating therapy with lansoprazole delayed-release capsules, amoxicillin capsules, and clarithromycin tablets careful inquiry should be made regarding previous hypersensitivity reactions to penicillins, cephalosporins, or other allergens. In the event of severe acute hypersensitivity reactions, such as anaphylaxis, and Henoch-Schonlein purpura lansoprazole delayed-release capsules, amoxicillin capsules, and clarithromycin tablets should be discontinued immediately and appropriate treatment should be urgently initiated.

Severe Cutaneous Adverse Reactions
Severe cutaneous adverse reactions (SCAR), including Stevens-Johnson syndrome (SJS), toxic epidermal necrolysis (TEN), drug reaction with eosinophilia and systemic symptoms (DRESS), and acute generalized exanthematous pustulosis (AGEP) have been reported with the components of lansoprazole delayed-release capsules, amoxicillin capsules, and clarithromycin tablets: lansoprazole, clarithromycin, and amoxicillin (see ADVERSE REACTIONS).

Monitor closely and discontinue lansoprazole delayed-release capsules, amoxicillin capsules, and clarithromycin tablets at the first signs of SCAR.

Drug-induced enterocolitis syndrome (DIES)

Drug-induced enterocolitis syndrome (DIES) has been reported with amoxicillin use (see ADVERSE REACTIONS), with most cases occurring in pediatric patients ≤18 years of age. DIES is a non-IgE mediated hypersensitivity reaction characterized by protracted vomiting occurring 1 to 4 hours after drug ingestion in the absence of skin or respiratory symptoms. DIES may be associated with pallor, lethargy, hypotension, shock, diarrhea within 24 hours after ingesting amoxicillin, and leukocytosis with neutrophilia. If DIES occurs, discontinue lansoprazole delayed-release capsules, amoxicillin capsules, and clarithromycin tablets and institute appropriate therapy.

Use in Pregnancy
CLARITHROMYCIN SHOULD NOT BE USED IN PREGNANT WOMEN EXCEPT IN CLINICAL CIRCUMSTANCES WHERE NO ALTERNATIVE THERAPY IS APPROPRIATE. IF PREGNANCY OCCURS WHILE TAKING CLARITHROMYCIN, THE PATIENT SHOULD BE INFORMED OF THE POTENTIAL HAZARD TO THE FETUS. CLARITHROMYCIN HAS DEMONSTRATED ADVERSE EFFECTS OF PREGNANCY OUTCOME AND/OR EMBRYO-FETAL DEVELOPMENT IN MONKEYS, RATS, MICE, AND RABBITS AT DOSES THAT PRODUCED PLASMA LEVELS TWO TO 17 TIMES THE SERUM LEVELS ACHIEVED IN HUMANS TREATED AT THE MAXIMUM RECOMMENDED HUMAN DOSES (see PRECAUTIONS, Pregnancy).

Hepatotoxicity

Hepatic dysfunction, including increased liver enzymes, and hepatocellular and/or cholestatic hepatitis, with or without jaundice, has been reported with clarithromycin. This hepatic dysfunction may be severe and is usually reversible. In some instances, hepatic failure with fatal outcome has been reported and generally has been associated with serious underlying diseases and/or concomitant medications. Symptoms of hepatitis can include anorexia, jaundice, dark urine, pruritus, or tender abdomen. Discontinue clarithromycin immediately if signs and symptoms of hepatitis occur.
QT Prolongation
Clarithromycin has been associated with prolongation of the QT interval and infrequent cases of arrhythmia. Cases of torsades de pointes have been spontaneously reported during postmarketing surveillance in patients receiving clarithromycin. Fatalities have been reported. Clarithromycin should be avoided in patients with ongoing proarrhythmic conditions such as uncorrected hypokalemia or hypomagnesemia, clinically significant bradycardia (see CONTRAINDICATIONS) and in patients receiving Class IA (quinidine, procainamide) or Class III (dofetilide, amiodarone, sotalol) antiarrhythmic agents. Elderly patients may be more susceptible to drug-associated effects on the QT interval.
Presence of Gastric Malignancy
In adults, symptomatic response to therapy with lansoprazole does not preclude the presence of gastric malignancy. Consider additional follow-up and diagnostic testing in adult patients who have a suboptimal response or an early symptomatic relapse after completing treatment with a PPI. In older patients, also consider an endoscopy.
Acute Interstitial Nephritis
Acute interstitial nephritis (AIN) has been observed in patients taking proton pump inhibitors (PPIs) including lansoprazole. Acute interstitial nephritis may occur at any point during PPI therapy and is generally attributed to an idiopathic hypersensitivity reaction. Discontinue lansoprazole if AIN develops (see CONTRAINDICATIONS).
Cutaneous and Systemic Lupus Erythematosus
Cutaneous lupus erythematosus (CLE) and systemic lupus erythematosus (SLE) have been reported in patients taking PPIs, including lansoprazole. These events have occurred as both new onset and an exacerbation of existing autoimmune disease. The majority of PPI-induced lupus erythematosus cases were CLE.
The most common form of CLE reported in patients treated with PPIs was subacute CLE (SCLE) and occurred within weeks to years after continuous drug therapy in patients ranging from infants to the elderly. Generally, histological findings were observed without organ involvement.
Systemic lupus erythematosus (SLE) is less commonly reported than CLE in patients receiving PPIs. PPI associated SLE is usually milder than non-drug induced SLE. Onset of SLE typically occurred within days to years after initiating treatment primarily in patients ranging from young adults to the elderly. The majority of patients presented with rash; however, arthralgia and cytopenia were also reported.
Avoid administration of PPIs for longer than medically indicated. If signs or symptoms consistent with CLE or SLE are noted in patients receiving Lansoprazole delayed-release capsules, amoxicillin capsules, and clarithromycin tablets, discontinue the drug and refer the patient to the appropriate specialist for evaluation. Most patients improve with discontinuation of the PPI alone in 4 to 12 weeks. Serological testing (e.g. ANA) may be positive and elevated serological test results may take longer to resolve than clinical manifestations
Drug Interactions
Serious adverse reactions have been reported in patients taking clarithromycin concomitantly with CYP3A4 substrates. These include colchicine toxicity with colchicine; rhabdomyolysis with simvastatin, lovastatin, and atorvastatin; hypoglycemia with disopyramide, toxicity with lurasidone, and hypotension and acute kidney injury with calcium channel blockers metabolized by CYP3A4 (e.g., verapamil, amlodipine, diltiazem, nifedipine). Most reports of acute kidney injury with calcium channel blockers metabolized by CYP3A4 involved elderly patients 65 years of age or older (see CONTRAINDICATIONS and PRECAUTIONS, Drug Interactions). Clarithromycin should be used with caution when administered concurrently with medications that induce the cytochrome CYP3A4 enzyme (see PRECAUTIONS, Drug Interactions).
Colchicine
Life-threatening and fatal drug interactions have been reported in patients treated with clarithromycin and colchicine. Clarithromycin is a strong CYP3A4 inhibitor and this interaction may occur while using both drugs at their recommended doses. If coadministration of clarithromycin and colchicine is necessary in patients with normal renal and hepatic function, the dose of colchicine should be reduced. Patients should be monitored for clinical symptoms of colchicine toxicity. Concomitant administration of clarithromycin and colchicine is contraindicated in patients with renal or hepatic impairment (see CONTRAINDICATIONS and PRECAUTIONS, Drug Interactions).
Benzodiazepines
Increased sedation and prolongation of sedation have been reported with concomitant administration of clarithromycin and triazolobenzodiazepines, such as triazolam, and midazolam.
Oral Hypoglycemic Agents/Insulin
The concomitant use of clarithromycin and oral hypoglycemic agents and/or insulin can result in significant hypoglycemia. With certain hypoglycemic drugs such as nateglinide, pioglitazone, repaglinide and rosiglitazone, inhibition of CYP3A enzyme by clarithromycin may be involved and could cause hypoglycemia when used concomitantly. Careful monitoring of glucose is recommended.
Oral Anticoagulants
There is a risk of serious hemorrhage and significant elevations in INR and prothrombin time when clarithromycin is co-administered with warfarin. INR and prothrombin times should be frequently monitored while patients are receiving clarithromycin and oral anticoagulants concurrently.
HMG-CoA Reductase Inhibitors (statins)
Concomitant use of clarithromycin with lovastatin or simvastatin is contraindicated (see CONTRAINDICATIONS) as these statins are extensively metabolized by CYP3A4, and concomitant treatment with clarithromycin increases their plasma concentration, which increases the risk of myopathy, including rhabdomyolysis. Cases of rhabdomyolysis have been reported in patients taking clarithromycin concomitantly with these statins. If treatment with clarithromycin cannot be avoided, therapy with lovastatin or simvastatin must be suspended during the course of treatment.
Caution should be exercised when prescribing clarithromycin with statins. In situations where the concomitant use of clarithromycin with atorvastatin or pravastatin cannot be avoided, atorvastatin dose should not exceed 20 mg daily and pravastatin dose should not exceed 40 mg daily. Use of a statin that is not dependent on CYP3A metabolism (e.g., fluvastatin) can be considered. It is recommended to prescribe the lowest registered dose if concomitant use cannot be avoided.

Antipsychotics

Clarithromycin is a strong CYP3A inhibitor. Clarithromycin may increase exposure of antipsychotic drugs that are CYP3A substrates including lurasidone, pimozide, quetiapine, which may increase the risk of adverse reactions including the risk of somnolence, orthostatic hypotension, altered mental status, neuroleptic malignant syndrome, or cardiac arrhythmias (QT prolongation, ventricular tachycardia, ventricular fibrillation, and torsades de pointes).

Interactions with Investigations for Neuroendocrine Tumors
Serum chromogranin A (CgA) levels increase secondary to drug-induced decreases in gastric acidity. The increased CgA level may cause false positive results in diagnostic investigations for neuroendocrine tumors. Healthcare providers should temporarily stop lansoprazole treatment at least 14 days before assessing CgA levels and consider repeating the test if initial CgA levels are high. If serial tests are performed (e.g., for monitoring), the same commercial laboratory should be used for testing, as reference ranges between tests may vary (see CLINICAL PHARMACOLOGY, Drug Interaction Studies).
Interaction with Methotrexate
Literature suggests that concomitant use of PPIs with methotrexate (primarily at high dose) may elevate and prolong serum levels of methotrexate and/or its metabolite, possibly leading to methotrexate toxicities. In high-dose methotrexate administration, a temporary withdrawal of the PPI may be considered in some patients (see CLINICAL PHARMACOLOGY, Drug Interaction Studies).
Clostridium difficile-Associated Diarrhea
Clostridium difficile associated diarrhea (CDAD) has been reported with use of nearly all antibacterial agents, including clarithromycin and/or amoxicillin, and may range in severity from mild diarrhea to fatal colitis. Treatment with antibacterial agents alters the normal flora of the colon leading to overgrowth of C. difficile.
C. difficile produces toxins A and B which contribute to the development of CDAD. Hypertoxin producing strains of C. difficile cause increased morbidity and mortality, as these infections can be refractory to antimicrobial therapy and may require colectomy. CDAD must be considered in all patients who present with diarrhea following antibiotic use. Careful medical history is necessary since CDAD has been reported to occur over two months after the administration of antibacterial agents.
If CDAD is suspected or confirmed, ongoing antibiotic use not directed against C. difficile may need to be discontinued. Appropriate fluid and electrolyte management, protein supplementation, antibiotic treatment of C. difficile, and surgical evaluation should be instituted as clinically indicated.
In addition, published observational studies suggest that PPI therapy, may be associated with an increased risk of CDAD, especially in hospitalized patients. This diagnosis should be considered for diarrhea that does not improve.

PRECAUTIONS

General

The possibility of superinfections with fungal or bacterial pathogens should be considered during therapy. If superinfections occur, lansoprazole delayed-release capsules, amoxicillin capsules, and clarithromycin tablets should be discontinued and appropriate therapy instituted.
Prescribing lansoprazole delayed-release capsules, amoxicillin capsules, and clarithromycin tablets either in the absence of a proven or strongly suspected bacterial infection is unlikely to provide benefit to the patient and increases the risk of the development of drug-resistant bacteria.
Clarithromycin is principally excreted via the liver and kidney. Clarithromycin may be administered without dosage adjustment to patients with hepatic impairment and normal renal function. However, in the presence of severe renal impairment with or without coexisting hepatic impairment, decreased dosage or prolonged dosing intervals may be appropriate.
Exacerbation of symptoms of myasthenia gravis and new onset of symptoms of myasthenic syndrome has been reported in patients receiving clarithromycin therapy.

Information for Patients

Each dose of lansoprazole delayed-release capsules, amoxicillin capsules, and clarithromycin tablets contain four pills: one dark blue and pink capsule (lansoprazole delayed-release capsules), two blue/pink hard gelatin capsules (amoxicillin) and one light yellow tablet (clarithromycin). Each dose should be taken twice per day before eating. Patients should be instructed to swallow each pill whole.
Lansoprazole delayed-release capsules, amoxicillin capsules, and clarithromycin tablets may interact with some drugs; therefore patients should be advised to report to their doctor the use of any other medications.
Patients should be counseled that antibacterial drugs including lansoprazole delayed-release capsules, amoxicillin capsules, and clarithromycin tablets should only be used to treat bacterial infections. They do not treat viral infections (e.g., the common cold). When lansoprazole delayed-release capsules, amoxicillin capsules, and clarithromycin tablets are prescribed to treat a bacterial infection, patients should be told that although it is common to feel better early in the course of therapy, the medication should be taken exactly as directed. Skipping doses or not completing the full course of therapy may (1) decrease the effectiveness of the immediate treatment and (2) increase the likelihood that bacteria will develop resistance and will not be treatable by lansoprazole delayed-release capsules, amoxicillin capsules, and clarithromycin tablets or other antibacterial drugs in the future.
Diarrhea is a common problem caused by antibiotics which usually ends when the antibiotic is discontinued. Sometimes after starting treatment with antibiotics, patients can develop watery and bloody stools (with or without stomach cramps and fever) even as late as two or more months after having taken the last dose of the antibiotic. If this occurs, patients should contact their physician as soon as possible.
Patients should be advised to immediately report and seek care for diarrhea that does not improve. This may be a sign of Clostridium difficile associated diarrhea (see WARNINGS).
Patients should be advised to immediately report and seek care for any cardiovascular or neurological symptoms including palpitations, dizziness, seizures, and tetany as these may be signs of hypomagnesemia (see WARNINGS).
Advise patients to report any symptoms associated with cutaneous or systemic lupus erythematosus (see WARNINGS).
Advise patients to report to their healthcare provider if they are taking rilpivirine-containing products or high-dose methotrexate (see WARNINGS).
Advise patients about the signs and symptoms of serious skin manifestations. Instruct patients to stop taking lansoprazole delayed-release capsules, amoxicillin capsules, and clarithromycin tablets immediately and promptly report the first signs or symptoms of skin rash, mucosal lesions, or any other sign of hypersensitivity.

Laboratory Tests

Amoxicillin
Periodic assessment of renal, hepatic, and hematopoietic function should be made during prolonged therapy.

Drug Interactions

No drug interaction studies have been conducted specifically with lansoprazole delayed-release capsules, amoxicillin capsules, and clarithromycin tablets. The following drug interactions are for the individual drug components: lansoprazole, amoxicillin, and clarithromycin. Therefore, the decision to adjust dosage should depend on the clinician’s assessment of among other things, the cumulative or net effect of the drug components of lansoprazole delayed-release capsules, amoxicillin capsules, and clarithromycin tablets.
Lansoprazole Delayed-Release Capsules
Tables 5 and 6 include drugs with clinically important drug interactions and interaction with diagnostics when administered concomitantly with lansoprazole delayed-release capsules and instructions for preventing or managing them.
Consult the labeling of concomitantly used drugs to obtain further information about interactions with PPIs.

Table 5. Clinically Relevant Interactions Affecting Drugs Coadministered with Lansoprazole Delayed-release Capsules and Interactions with Diagnostics
Antiretrovirals
Clinical Impact: | The effect of PPIs on antiretroviral drugs is variable. The clinical importance and the mechanisms behind these interactions are not always known.; - Decreased exposure of some antiretroviral drugs (e.g., rilpivirine, atazanavir, and nelfinavir) when used concomitantly with lansoprazole may reduce antiviral effect and promote the development of drug resistance. - Increased exposure of other antiretroviral drugs (e.g., saquinavir) when used concomitantly with lansoprazole may increase toxicity of the antiretroviral drugs. - There are other antiretroviral drugs which do not result in clinically relevant interactions with lansoprazole.
Intervention: | Rilpivirine-containing products: Concomitant use with lansoprazole is contraindicated (see CONTRAINDICATIONS). See prescribing information. Atazanavir: See prescribing information for atazanavir for dosing information. Nelfinavir: Avoid concomitant use with lansoprazole. See prescribing information for nelfinavir. Saquinavir: See the prescribing information for saquinavir and monitor for potential saquinavir toxicities. Other antiretrovirals: See prescribing information.
Warfarin
Clinical Impact: | Increased INR and prothrombin time in patients receiving PPIs and warfarin concomitantly. Increases in INR and prothrombin time may lead to abnormal bleeding and even death.
Intervention: | Monitor INR and prothrombin time. Dose adjustment of warfarin may be needed to maintain target INR range. See prescribing information for warfarin.
Methotrexate
Clinical Impact: | Concomitant use of PPIs with methotrexate (primarily at high dose) may elevate and prolong serum concentrations of methotrexate and/or its metabolite hydroxymethotrexate, possibly leading to methotrexate toxicities. No formal drug interaction studies of high-dose methotrexate with PPIs have been conducted (see WARNINGS).
Intervention: | A temporary withdrawal of lansoprazole may be considered in some patients receiving high-dose methotrexate.
Digoxin
Clinical Impact: | Potential for increased exposure of digoxin.
Intervention: | Monitor digoxin concentrations. Dose adjustment of digoxin may be needed to maintain therapeutic drug concentrations. See prescribing information for digoxin.
Theophylline
Clinical Impact: | Increased clearance of theophylline (see CLINICAL PHARMACOLOGY).
Intervention: | Individual patients may require additional titration of their theophylline dosage when lansoprazole is started or stopped to ensure clinically effective blood concentrations.
Drugs Dependent on Gastric pH for Absorption (e.g., iron salts, erlotinib, dasatinib, nilotinib, mycophenolate mofetil, ketoconazole/itraconazole)
Clinical Impact: | Lansoprazole can reduce the absorption of other drugs due to its effect on reducing intragastric acidity.
Intervention: | Mycophenolate mofetil (MMF): Coadministration of PPIs in healthy subjects and in transplant patients receiving MMF has been reported to reduce the exposure to the active metabolite, mycophenolic acid (MPA), possibly due to a decrease in MMF solubility at an increased gastric pH. The clinical relevance of reduced MPA exposure on organ rejection has not been established in transplant patients receiving lansoprazole delayed-release capsules and MMF. Use lansoprazole delayed-release capsules with caution in transplant patients receiving MMF. See the prescribing information for other drugs dependent on gastric pH for absorption.
Combination Therapy with Clarithromycin and Amoxicillin
Clinical Impact: | Concomitant administration of clarithromycin with other drugs can lead to serious adverse reactions, including potentially fatal arrhythmias, and are contraindicated. Amoxicillin also has drug interactions.
Intervention: | - See CONTRAINDICATIONS, WARNINGS and PRECAUTIONS in prescribing information for clarithromycin. - See Drug Interactions in prescribing information for amoxicillin.
Tacrolimus
Clinical Impact: | Potentially increased exposure of tacrolimus, especially in transplant patients who are intermediate or poor metabolizers of CYP2C19.
Intervention: | Monitor tacrolimus whole blood trough concentrations. Dose adjustment of tacrolimus may be needed to maintain therapeutic drug concentrations. See prescribing information for tacrolimus.
Interactions with Investigations of Neuroendocrine Tumors
Clinical Impact: | CgA levels increase secondary to PPI-induced decreases in gastric acidity. The increased CgA level may cause false positive results in diagnostic investigations for neuroendocrine tumors (see WARNINGS, CLINICAL PHARMACOLOGY).
Intervention: | Temporarily stop lansoprazole treatment at least 14 days before assessing CgA levels and consider repeating the test if initial CgA levels are high. If serial tests are performed (e.g., for monitoring), the same commercial laboratory should be used for testing, as reference ranges between tests may vary.
Interaction with Secretin Stimulation Test
Clinical Impact: | Hyper-response in gastrin secretion in response to secretin stimulation test, falsely suggesting gastrinoma.
Intervention: | Temporarily stop lansoprazole treatment at least 28 days before assessing to allow gastrin levels to return to baseline (see CLINICAL PHARMACOLOGY).
False Positive Urine Tests for THC
Clinical Impact: | There have been reports of false positive urine screening tests for tetrahydrocannabinol (THC) in patients receiving PPIs.
Intervention: | An alternative confirmatory method should be considered to verify positive results.

Table 6. Clinically Relevant Interactions Affecting Lansoprazole Delayed-release Capsules When Coadministered with Other Drugs
CYP2C19 OR CYP3A4 Inducers
Clinical Impact: | Decreased exposure of lansoprazole when used concomitantly with strong inducers (see CLINICAL PHARMACOLOGY).
Intervention: | St John's Wort, rifampin: Avoid concomitant use with lansoprazole. Ritonavir-containing products: See prescribing information.
CYP2C19 or CYP3A4 Inhibitors
Clinical Impact: | Increased exposure of lansoprazole is expected when used concomitantly with strong inhibitors (see CLINICAL PHARMACOLOGY).
Intervention: | Voriconazole: See prescribing information.
Sucralfate
Clinical Impact: | Decreased and delayed absorption of lansoprazole (see CLINICAL PHARMACOLOGY).
Intervention: | Take lansoprazole delayed-release capsules at least 30 minutes prior to sucralfate (see CLINICAL PHARMACOLOGY).

Amoxicillin
Probenecid
Probenecid decreases the renal tubular secretion of amoxicillin. Concurrent use of amoxicillin and probenecid may result in increased and prolonged blood levels of amoxicillin.
Antibiotics
Chloramphenicol, macrolides, sulfonamides, and tetracyclines may interfere with bactericidal effects of penicillin. This has been demonstrated in vitro; however, the clinical significance of this interaction is not well documented.
Amoxicillin may affect the gut flora, leading to lower estrogen reabsorption and reduced efficacy of combined oral estrogen/progesterone contraceptives.

Table 7. Clinically Significant Drug Interactions with Clarithromycin Tablets
Drugs That Are Affected By Clarithromycin tablets
Drug(s) with Pharmacokinetics Affected by Clarithromycin tablets | Recommendation | Comments
Antiarrhythmics:
Disopyramide Quinidine Dofetilide Amiodarone Sotalol Procainamide | Not Recommended | Disopyramide, Quinidine: There have been postmarketing reports of torsades de pointes occurring with concurrent use of clarithromycin and quinidine or disopyramide. Electrocardiograms should be monitored for QTc prolongation during coadministration of clarithromycin with these drugs (see WARNINGS). Serum concentrations of these medications should also be monitored. There have been spontaneous or published reports of CYP3A based interactions of clarithromycin with disopyramide and quinidine. There have been postmarketing reports of hypoglycemia with the concomitant administration of clarithromycin and disopyramide. Therefore, blood glucose levels should be monitored during concomitant administration of clarithromycin and disopyramide.
Digoxin | Use With Caution | Digoxin: Digoxin is a substrate for P-glycoprotein (Pgp) and clarithromycin is known to inhibit Pgp. When clarithromycin and digoxin are coadministered, inhibition of Pgp by clarithromycin may lead to increased exposure of digoxin. Elevated digoxin serum concentrations in patients receiving clarithromycin and digoxin concomitantly have been reported in postmarketing surveillance. Some patients have shown clinical signs consistent with digoxin toxicity, including potentially fatal arrhythmias. Monitoring of serum digoxin concentrations should be considered, especially for patients with digoxin concentrations in the upper therapeutic range.
Oral Anticoagulants:
Warfarin | Use With Caution | Oral anticoagulants: Spontaneous reports in the postmarketing period suggest that concomitant administration of clarithromycin and oral anticoagulants may potentiate the effects of the oral anticoagulants. Prothrombin times should be carefully monitored while patients are receiving clarithromycin and oral anticoagulants simultaneously (see WARNINGS).
Antiepileptics:
Carbamazepine | Use With Caution | Carbamazepine: Concomitant administration of single doses of clarithromycin and carbamazepine has been shown to result in increased plasma concentrations of carbamazepine. Blood level monitoring of carbamazepine may be considered. Increased serum concentrations of carbamazepine were observed in clinical trials with clarithromycin. There have been spontaneous or published reports of CYP3A based interactions of clarithromycin with carbamazepine.
Antifungals:
Itraconazole | Use With Caution | Itraconazole: Both clarithromycin and itraconazole are substrates and inhibitors of CYP3A, potentially leading to a bi-directional drug interaction when administered concomitantly (see also Itraconazole under "Drugs That Affect Clarithromycin Tablets" in the table below). Clarithromycin may increase the plasma concentrations of itraconazole. Patients taking itraconazole and clarithromycin concomitantly should be monitored closely for signs or symptoms of increased or prolonged adverse reactions.
Fluconazole | No Dose Adjustment | Fluconazole: No dosage adjustment of clarithromycin is necessary when coadministered with fluconazole.
Anti-Gout Agents:
Colchicine (in patients with renal or hepatic impairment) | Contraindicated | Colchicine: Colchicine is a substrate for both CYP3A and the efflux transporter, P-glycoprotein (Pgp). Clarithromycin and other macrolides are known to inhibit CYP3A and Pgp. The dose of colchicine should be reduced when coadministered with clarithromycin in patients with normal renal and hepatic function (see CONTRAINDICATIONS, WARNINGS).
Colchicine (in patients with normal renal and hepatic function) | Use With Caution | Colchicine: Colchicine is a substrate for both CYP3A and the efflux transporter, P-glycoprotein (Pgp). Clarithromycin and other macrolides are known to inhibit CYP3A and Pgp. The dose of colchicine should be reduced when coadministered with clarithromycin in patients with normal renal and hepatic function (see CONTRAINDICATIONS, WARNINGS).
Antipsychotics:
Pimozide | Contraindicated | Pimozide: (see CONTRAINDICATIONS).
Lurasidone | Contraindicated | Lurasidone: (see CONTRAINDICATIONS).
Quetiapine | Contraindicated | Quetiapine: Quetiapine is a substrate for CYP3A4, which is inhibited by clarithromycin. Coadministration with clarithromycin could result in increased quetiapine exposure and possible quetiapine related toxicities. There have been postmarketing reports of somnolence, orthostatic hypotension, altered state of consciousness, neuroleptic malignant syndrome, and QT prolongation during concomitant administration. Refer to quetiapine prescribing information for recommendations on dose reduction if coadministered with CYP3A4 inhibitors such as clarithromycin.
Antispasmodics:
Tolterodine (patients deficient in CYP2D6 activity) | Use With Caution | Tolterodine: The primary route of metabolism for tolterodine is via CYP2D6. However, in a subset of the population devoid of CYP2D6, the identified pathway of metabolism is via CYP3A. In this population subset, inhibition of CYP3A results in significantly higher serum concentrations of tolterodine. Tolterodine 1 mg twice daily is recommended in patients deficient in CYP2D6 activity (poor metabolizers) when coadministered with clarithromycin.
Antivirals:
Atazanavir | Use With Caution | Atazanavir: Both clarithromycin and atazanavir are substrates and inhibitors of CYP3A, and there is evidence of a bi-directional drug interaction (see Atazanavir under "Drugs That Affect Clarithromycin Tablets" in the table below).
Saquinavir (in patients with decreased renal function) |  | Saquinavir: Both clarithromycin and saquinavir are substrates and inhibitors of CYP3A and there is evidence of a bi-directional drug interaction (see Saquinavir under “Drugs That Affect Clarithromycin Tablets” in the table below).
Ritonavir Etravirine |  | Ritonavir, Etravirine: (see Ritonavir and Etravirine under "Drugs That Affect Clarithromycin Tablets" in the table below).
Maraviroc |  | Maraviroc: Clarithromycin may result in increases in maraviroc exposures by inhibition of CYP3A metabolism. See Selzentry® prescribing information for dose recommendation when given with strong CYP3A inhibitors such as clarithromycin.
Boceprevir (in patients with normal renal function) | No Dose Adjustment | Boceprevir: Both clarithromycin and boceprevir are substrates and inhibitors of CYP3A, potentially leading to a bi-directional drug interaction when coadministered. No dose adjustments are necessary for patients with normal renal function (see Victrelis® prescribing information).
Didanosine | No Dose Adjustment
Zidovudine |  | Zidovudine: Simultaneous oral administration of clarithromycin immediate-release tablets and zidovudine to HIV-infected adult patients may result in decreased steady-state zidovudine concentrations. Administration of clarithromycin and zidovudine should be separated by at least two hours. The impact of coadministration of clarithromycin extended-release tablets or granules and zidovudine has not been evaluated.
Calcium Channel Blockers:
Verapamil | Use With Caution | Verapamil: Hypotension, bradyarrhythmias, and lactic acidosis have been observed in patients receiving concurrent verapamil (see WARNINGS).
Amlodipine Diltiazem |  | Amlodipine, Diltiazem: (see WARNINGS).
Nifedipine |  | Nifedipine: Nifedipine is a substrate for CYP3A. Clarithromycin and other macrolides are known to inhibit CYP3A. There is potential of CYP3A-mediated interaction between nifedipine and clarithromycin. Hypotension and peripheral edema were observed when clarithromycin was taken concomitantly with nifedipine (see WARNINGS).
Ergot Alkaloids:
Ergotamine Dihydroergotamine | Contraindicated | Ergotamine, Dihydroergotamine: Postmarketing reports indicate that coadministration of clarithromycin with ergotamine or dihydroergotamine has been associated with acute ergot toxicity characterized by vasospasm and ischemia of the extremities and other tissues including the central nervous system (see CONTRAINDICATIONS).
Gastroprokinetic Agents:
Cisapride | Contraindicated | Cisapride: (see CONTRAINDICATIONS).
HMG-CoA Reductase Inhibitors:
Lovastatin Simvastatin | Contraindicated | Lovastatin, Simvastatin, Atorvastatin, Pravastatin, Fluvastatin: (see CONTRAINDICATIONS, WARNINGS).
Atorvastatin Pravastatin | Use With Caution
Fluvastatin | No Dose Adjustment
Hypoglycemic Agents:
Nateglinide Pioglitazone Repaglinide Rosiglitazone | Use With Caution | Nateglinide, Pioglitazone, Repaglinide, Rosiglitazone: (see WARNINGS, ADVERSE REACTIONS).
Insulin |  | Insulin: (see WARNINGS, ADVERSE REACTIONS).
Immunosuppressants:
Cyclosporine | Use With Caution | Cyclosporine: There have been spontaneous or published reports of CYP3A based interactions of clarithromycin with cyclosporine.
Tacrolimus |  | Tacrolimus: There have been spontaneous or published reports of CYP3A based interactions of clarithromycin with tacrolimus.
Phosphodiesterase Inhibitors:
Sildenafil Tadalafil Vardenafil | Use With Caution | Sildenafil, Tadalafil, Vardenafil: Each of these phosphodiesterase inhibitors is primarily metabolized by CYP3A, and CYP3A will be inhibited by concomitant administration of clarithromycin. Coadministration of clarithromycin with sildenafil, tadalafil, or vardenafil will result in increased exposure of these phosphodiesterase inhibitors. Coadministration of these phosphodiesterase inhibitors with clarithromycin is not recommended. Increased systemic exposure of these drugs may occur with clarithromycin; reduction of dosage for phosphodiesterase inhibitors should be considered (see their respective prescribing information).
Proton Pump Inhibitors:
Omeprazole | No Dose Adjustment | Omeprazole: The mean 24 hour gastric pH value was 5.2 when omeprazole was administered alone and 5.7 when coadministered with clarithromycin as a result of increased omeprazole exposures (see also Omeprazole under "Drugs That Affect Clarithromycin Tablets" in the table below).
Xanthine Derivatives:
Theophylline | Use With Caution | Theophylline: Clarithromycin use in patients who are receiving theophylline may be associated with an increase of serum theophylline concentrations. Monitoring of serum theophylline concentrations should be considered for patients receiving high doses of theophylline or with baseline concentrations in the upper therapeutic range.
Triazolobenzodiazepines and Other Related Benzodiazepines:
Midazolam | Use With Caution | Midazolam: When oral midazolam is coadministered with clarithromycin, dose adjustments may be necessary and possible prolongation and intensity of effect should be anticipated (see WARNINGS).
Alprazolam Triazolam |  | Triazolam, Alprazolam: Caution and appropriate dose adjustments should be considered when triazolam or alprazolam is coadministered with clarithromycin. There have been postmarketing reports of drug interactions and central nervous system (CNS) effects (e.g., somnolence and confusion) with the concomitant use of clarithromycin and triazolam. Monitoring the patient for increased CNS pharmacological effects is suggested. In postmarketing experience, erythromycin has been reported to decrease the clearance of triazolam and midazolam, and thus, may increase the pharmacologic effect of these benzodiazepines.
Temazepam Nitrazepam Lorazepam | No Dose Adjustment | Temazepam, Nitrazepam, Lorazepam: For benzodiazepines which are not metabolized by CYP3A (e.g., temazepam, nitrazepam, lorazepam), a clinically important interaction with clarithromycin is unlikely.
Cytochrome P450 Inducers:
Rifabutin | Use With Caution | Rifabutin: Concomitant administration of rifabutin and clarithromycin resulted in an increase in rifabutin, and decrease in clarithromycin serum levels together with an increased risk of uveitis (see Rifabutin under "Drugs That Affect Clarithromycin Tablets" in the table below).
Other Drugs Metabolized by CYP3A:
Alfentanil Bromocriptine Cilostazol Methylprednisolone Vinblastine Phenobarbital St. John's Wort | Use With Caution | There have been spontaneous or published reports of CYP3A based interactions of clarithromycin with alfentanil, methylprednisolone, cilostazol, bromocriptine, vinblastine, phenobarbital, and St. John's Wort.
Other Drugs Metabolized by CYP450 Isoforms Other than CYP3A:
Hexobarbital Phenytoin Valproate | Use With Caution | There have been postmarketing reports of interactions of clarithromycin with drugs not thought to be metabolized by CYP3A, including hexobarbital, phenytoin, and valproate.
Drugs That Affect Clarithromycin Tablets
Drug(s) that Affect the Pharmacokinetics of Clarithromycin Tablets | Recommendation | Comments
Antifungals:
Itraconazole | Use With Caution | Itraconazole: Itraconazole may increase the plasma concentrations of clarithromycin. Patients taking itraconazole and clarithromycin concomitantly should be monitored closely for signs or symptoms of increased or prolonged adverse reactions (see also Itraconazole under "Drugs That Are Affected By Clarithromycin Tablets" in the table above).
Antivirals:
Atazanavir | Use With Caution | Atazanavir: When clarithromycin is coadministered with atazanavir, the dose of clarithromycin should be decreased by 50%. Since concentrations of 14-OH clarithromycin are significantly reduced when clarithromycin is coadministered with atazanavir, alternative antibacterial therapy should be considered for indications other than infections due to Mycobacterium avium complex. Doses of clarithromycin greater than 1000 mg per day should not be coadministered with protease inhibitors.
Ritonavir (in patients with decreased renal function) |  | Ritonavir: Since concentrations of 14-OH clarithromycin are significantly reduced when clarithromycin is coadministered with ritonavir, alternative antibacterial therapy should be considered for indications other than infections due to Mycobacterium avium. Doses of clarithromycin greater than 1000 mg per day should not be coadministered with protease inhibitors.
Saquinavir (in patients with decreased renal function) |  | Saquinavir: When saquinavir is coadministered with ritonavir, consideration should be given to the potential effects of ritonavir on clarithromycin (refer to ritonavir above).
Etravirine |  | Etravirine: Clarithromycin exposure was decreased by etravirine; however, concentrations of the active metabolite, 14-OH-clarithromycin, were increased. Because 14-OH-clarithromycin has reduced activity against Mycobacterium avium complex (MAC), overall activity against this pathogen may be altered; therefore alternatives to clarithromycin should be considered for the treatment of MAC.
Saquinavir (in patients with normal renal function) Ritonavir (in patients with normal renal function) | No Dose Adjustment
Proton Pump Inhibitors:
Omeprazole | Use With Caution | Omeprazole: Clarithromycin concentrations in the gastric tissue and mucus were also increased by concomitant administration of omeprazole.
Miscellaneous Cytochrome P450 Inducers:
Efavirenz Nevirapine Rifampicin Rifabutin Rifapentine | Use With Caution | Inducers of CYP3A enzymes, such as efavirenz, nevirapine, rifampicin, rifabutin, and rifapentine will increase the metabolism of clarithromycin, thus decreasing plasma concentrations of clarithromycin, while increasing those of 14-OH-clarithromycin. Since the microbiological activities of clarithromycin and 14-OH-clarithromycin are different for different bacteria, the intended therapeutic effect could be impaired during concomitant administration of clarithromycin and enzyme inducers. Alternative antibacterial treatment should be considered when treating patients receiving inducers of CYP3A. There have been spontaneous or published reports of CYP3A based interactions of clarithromycin with rifabutin (see Rifabutin under "Drugs That Are Affected By Clarithromycin Tablets" in the table above).

Drug/Laboratory Test Interactions

High urine concentrations of ampicillin may result in false-positive reactions when testing for the presence of glucose in urine using CLINITEST, Benedict's Solution or Fehling's Solution. Since this effect may also occur with amoxicillin, it is recommended that glucose tests based on enzymatic glucose oxidase reactions (such as CLINISTIX) be used.
Following administration of ampicillin to pregnant women, a transient decrease in plasma concentration of total conjugated estriol, estriol-glucuronide, conjugated estrone, and estradiol has been noted. This effect may also occur with amoxicillin.

Carcinogenesis, Mutagenesis, Impairment of Fertility

Lansoprazole Delayed-Release Capsules
In two 24-month carcinogenicity studies, Sprague-Dawley rats were treated with oral lansoprazole at doses of 5 to 150 mg/kg/day, about 0.5 to 20 times the recommended human dose of 60 mg/day, based on body surface area (BSA). Lansoprazole produced dose-related gastric enterochromaffin-like (ECL) cell hyperplasia and ECL cell carcinoids in both male and female rats. The incidences of intestinal metaplasia of the gastric epithelium were also increased in both sexes. In male rats, lansoprazole produced a dose-related increase in the incidence of testicular interstitial cell adenomas at doses two to 20 times the recommended human dose of 60 mg/day based on BSA.
In a 24-month carcinogenicity study, CD-1 mice were treated with oral lansoprazole at doses of 15 to 600 mg/kg/day (one to 40 times the recommended human dose of 60 mg/day based on BSA comparisons). Lansoprazole produced a dose-related increased incidence of gastric ECL cell hyperplasia. The incidence of liver tumors (hepatocellular adenoma plus carcinoma) was increased in male mice (at doses 20 to 40 times the recommended human dose of 60 mg/day based on BSA) and in female mice (treated at doses ten to 40 times the recommended human dose based on BSA). Lansoprazole treatment produced adenoma of rete testis in male mice receiving doses five to 40 times the recommended human dose of 60 mg/day based on BSA.
A 26 week p53 (+/-) transgenic mouse carcinogenicity study was not positive.
Lansoprazole was positive in the Ames test and the in vitro human lymphocyte chromosomal aberration assay. Lansoprazole was not genotoxic in the ex vivo rat hepatocyte unscheduled DNA synthesis (UDS) test, the in vivo mouse micronucleus test, or the rat bone marrow cell chromosomal aberration test.
Lansoprazole at oral doses up to 150 mg/kg/day (20 times the recommended human dose of 60 mg/day based on BSA) was found to have no effect on fertility and reproductive performance of male and female rats.
Amoxicillin
Long-term studies in animals have not been performed to evaluate the mutagenic or carcinogenic potential of amoxicillin alone. A 4:1 mixture of amoxicillin and potassium clavulanate was non-mutagenic in the Ames bacterial mutation assay, and the yeast gene conversion assay. The amoxicillin/potassium clavulanate mixture was also negative in the mouse micronucleus test, and in the dominant lethal assay in mice, but was weakly positive in the mouse lymphoma assay. In a multi-generation reproduction study in rats, no impairment of fertility or other adverse reproductive effects were seen at doses up to 500 mg/kg, approximately three times the human dose based on BSA comparisons.
Clarithromycin
The following in vitro mutagenicity tests have been conducted with clarithromycin:
Salmonella/Mammalian Microsomes Test
Bacterial Induced Mutation Frequency Test
In Vitro Chromosome Aberration Test
Rat Hepatocyte DNA Synthesis Assay
Mouse Lymphoma Assay
Mouse Dominant Lethal Study
Mouse Micronucleus Test
All tests had negative results except the In Vitro Chromosome Aberration Test which was weakly positive in one test and negative in another.
In addition, a Bacterial Reverse-Mutation Test (Ames Test) has been performed on clarithromycin metabolites with negative results.
Fertility and reproduction studies have shown that daily doses of up to 160 mg/kg/day (1.3 times the recommended maximum human dose based on mg/m^2) to male and female rats caused no adverse effects on the estrous cycle, fertility, parturition, or number and viability of offspring. Plasma levels in rats after 150 mg/kg/day were two times the human serum levels.
In the 150 mg/kg/day monkey studies, plasma levels were three times the human serum levels. When given orally at 150 mg/kg/day (2.4 times the recommended maximum human dose based on mg/m^2), clarithromycin was shown to produce embryonic loss in monkeys. This effect has been attributed to marked maternal toxicity of the drug at this high dose.
In rabbits, in utero fetal loss occurred at an intravenous dose of 33 mg/m^2, which is 17 times less than the maximum proposed human oral daily dose of 618 mg/m^2 .
Long-term studies in animals have not been performed to evaluate the carcinogenic potential of clarithromycin.

Pregnancy

Teratogenic Effects
Pregnancy Category C
Category C is based on the pregnancy category for clarithromycin.
There are no adequate and well-controlled studies of lansoprazole, clarithromycin or amoxicillin (used separately or together) in pregnant women. Lansoprazole delayed-release capsules, amoxicillin capsules, and clarithromycin tablets should be used during pregnancy only if the potential benefit justifies the potential risk to the fetus and there is no appropriate alternative therapy (see WARNINGS).
Lansoprazole

No adverse effects on embryo-fetal development occurred in studies performed in pregnant rats at oral lansoprazole doses up to 150 mg/kg/day (40 times the recommended human dose [30 mg/day] based on body surface area) administered during organogenesis and pregnant rabbits at oral lansoprazole doses up to 30 mg/kg/day (16 times the recommended human dose based on body surface area) administered during organogenesis.

A pre- and postnatal developmental toxicity study in rats with additional endpoints to evaluate bone development was performed with lansoprazole at oral doses of 10 to 100 mg/kg/day (0.7 to 6.4 times the maximum recommended human lansoprazole dose of 30 mg based on AUC [area under the plasma concentration-time curve]) administered during organogenesis through lactation. Maternal effects observed at 100 mg/kg/day (6.4 times the maximum recommended human lansoprazole dose of 30 mg based on AUC) included increased gestation period, decreased body weight gain during gestation, and decreased food consumption. The number of stillbirths was increased at this dose, which may have been secondary to maternal toxicity. Body weight of pups was reduced at 100 mg/kg/day starting on postnatal Day 11. Femur weight, femur length, and crown-rump length were reduced at 100 mg/kg/day on postnatal Day 21. Femur weight was still decreased in the 100 mg/kg/day group at age 17 to 18 weeks. Growth plate thickness was decreased in the 100 mg/kg/day males on postnatal Day 21, and was increased in the 30 and 100 mg/kg/day males at age 17 to 18 weeks. The effects on bone parameters were associated with reduction in body weight gain.

Amoxicillin

Reproduction studies with amoxicillin have been performed in mice and rats at doses up to ten times the human dose and revealed no evidence of impaired fertility or harm to the fetus.

Clarithromycin

Four teratogenicity studies in rats with clarithromycin (three with oral doses and one with intravenous doses up to 160 mg/kg/day administered during the period of major organogenesis) and two in rabbits at oral doses up to 125 mg/kg/day (approximately two times the recommended maximum human dose based on mg/m^2) or intravenous doses of 30 mg/kg/day administered during gestation days six to 18 failed to demonstrate any teratogenicity from clarithromycin. Two additional oral studies in a different rat strain at similar doses and similar conditions demonstrated a low incidence of cardiovascular anomalies at doses of 150 mg/kg/day administered during gestation days six to 15. Plasma levels after 150 mg/kg/day were two times the human serum levels. Four studies in mice revealed a variable incidence of cleft palate following oral doses of 1000 mg/kg/day (two and four times the recommended maximum human dose based on mg/m^2, respectively) during gestation days six to 15. Cleft palate was also seen at 500 mg/kg/day. The 1000 mg/kg/day exposure resulted in plasma levels 17 times the human serum levels. In monkeys, an oral dose of 70 mg/kg/day (an approximate equidose of the recommended maximum human dose based on mg/m^2) produced fetal growth retardation at plasma levels that were two times the human serum levels.

Labor and Delivery

Oral ampicillin-class antibiotics are poorly absorbed during labor. Studies in guinea pigs showed that intravenous administration of ampicillin slightly decreased the uterine tone and frequency of contractions, but moderately increased the height and duration of contractions. However, it is not known whether use of these drugs in humans during labor or delivery has immediate or delayed adverse effects on the fetus, prolongs the duration of labor, or increases the likelihood that forceps delivery or other obstetrical intervention or resuscitation of the newborn will be necessary.

Nursing Mothers

Lansoprazole and its metabolites are excreted in the milk of rats. It is not known whether lansoprazole is excreted in human milk. Because of the potential for serious adverse reactions in nursing infants from lansoprazole delayed-release capsules, amoxicillin capsules, and clarithromycin tablets, and the potential for tumorigenicity shown for lansoprazole in rat carcinogenicity studies, a decision should be made whether to discontinue nursing or to discontinue lansoprazole delayed-release capsules, amoxicillin capsules, and clarithromycin tablets, taking into account the importance of the therapy to the mother.
Penicillins have been shown to be excreted in human milk. Amoxicillin use by nursing mothers may lead to sensitization of infants. Caution should be exercised when amoxicillin is administered to a nursing woman.
Clarithromycin and its active metabolite 14-hydroxy clarithromycin are excreted in human milk. Serum and milk samples were obtained after three days of treatment, at steady state, from one published study of 12 lactating women who were taking clarithromycin 250 mg orally twice daily. Based on the limited data from this study, and assuming milk consumption of 150 mL/kg/day, an exclusively human milk-fed infant would receive an estimated average of 136 mcg/kg/day of clarithromycin and its active metabolite, with this maternal dosage regimen. This is less than 2% of the maternal weight-adjusted dose (7.8 mg/kg/day, based on the average maternal weight of 64 kg), and less than 1% of the pediatric dose (15 mg/kg/day) for children greater than six months of age.
A prospective observational study of 55 breastfed infants of mothers taking a macrolide antibiotic (six were exposed to clarithromycin) were compared to 36 breastfed infants of mothers taking amoxicillin. Adverse reactions were comparable in both groups. Adverse reactions occurred in 12.7% of infants exposed to macrolides and included rash, diarrhea, loss of appetite, and somnolence.
Caution should be exercised when clarithromycin is administered to nursing women. The development and health benefits of human milk feeding should be considered along with the mother's clinical need for clarithromycin and any potential adverse effects on the human milk-fed child from the drug or from the underlying maternal condition.

Pediatric Use

The safety and effectiveness of lansoprazole delayed-release capsules, amoxicillin capsules, and clarithromycin tablets in pediatric patients infected with H. pylori have not been established.
Juvenile Animal Toxicity Data

In a juvenile rat study, adverse effects on bone growth and development and heart valves were observed at lansoprazole doses higher than the maximum recommended equivalent human dose.

An eight-week oral toxicity study with a four-week recovery phase was conducted in juvenile rats, with lansoprazole administered from postnatal Day 7 (age equivalent to neonatal humans) through 62 (age equivalent to approximately 14 years in humans) at doses of 40 to 500 mg/kg/day (about 1.2 to 12 times the daily pediatric dose of 15 mg in children age one to 11 years weighing 30 kg or less, based on AUC).

Heart valve thickening occurred at a dose of 500 mg/kg/day (approximately 12 times the daily dose of 15 mg in pediatric patients age one to 11 years weighing 30 kg or less, based on AUC). Heart valve thickening was not observed at the next lower dose (250 mg/kg/day) and below. The findings trended towards reversibility after a four-week drug-free recovery period. The relevance of heart valve thickening in this study to pediatric patients less than approximately 12 years of age is unknown. These findings are not relevant for patients 12 years of age and older. No effects on heart valves were observed in a 13-week intravenous toxicity study of lansoprazole in adolescent rats (approximately 12 years human age equivalence) at systemic exposures similar to those achieved in the eight-week oral toxicity study in juvenile (neonatal) rats.

In the eight-week oral toxicity study, doses equal to or greater than 100 mg/kg/day (about 2.5 times the daily pediatric dose of 15 mg in children age one to 11 years weighing 30 kg or less, based on AUC) produced delayed growth, with impairment of weight gain observed as early as postnatal Day 10 (age equivalent to neonatal humans). At the end of treatment, the signs of impaired growth at 100 mg/kg/day and higher included reductions in body weight (14% to 44% compared to controls), absolute weight of multiple organs, femur weight, femur length, and crown-rump length. Femoral growth plate thickness was reduced only in males and only at the 500 mg/kg/day dose. The effects related to delayed growth persisted through the end of the 4- week recovery period. Longer term data were not collected.

Geriatric Use

Elderly patients may suffer from asymptomatic renal and hepatic dysfunction. Care should be taken when administering lansoprazole delayed-release capsules, amoxicillin capsules, and clarithromycin tablets to this patient population.
An analysis of clinical studies of amoxicillin was conducted to determine whether subjects aged 65 and over respond differently from younger subjects. These analyses have not identified differences in responses between the elderly and younger patients, but a greater sensitivity of some older individuals cannot be ruled out.
Amoxicillin is known to be substantially excreted by the kidney, and the risk of toxic reactions to this drug may be greater in patients with impaired renal function. Because elderly patients are more likely to have decreased renal function, care should be taken in dose selection, and it may be useful to monitor renal function.
In a steady-state study in which healthy elderly subjects (age 65 to 81 years old) were given 500 mg of clarithromycin every 12 hours, the maximum serum concentrations and area under the curves of clarithromycin and 14-OH clarithromycin were increased compared to those achieved in healthy young adults. These changes in pharmacokinetics parallel known age-related decreases in renal function. In clinical trials of clarithromycin, elderly patients did not have an increased incidence of adverse events when compared to younger patients. Dosage adjustment should be considered in elderly patients with severe renal impairment. Elderly patients may be more susceptible to development of torsades de pointes arrhythmias than younger patients (see WARNINGS and PRECAUTIONS).
Most reports of acute kidney injury with calcium channel blockers metabolized by CYP3A4 (e.g., verapamil, amlodipine, diltiazem, nifedipine) involved elderly patients 65 years of age or older (see WARNINGS).

ADVERSE REACTIONS

LANSOPRAZOLE DELAYED-RELEASE CAPSULES, AMOXICILLIN CAPSULES, AND CLARITHROMYCIN TABLETS
Because clinical trials are conducted under widely varying conditions, adverse reaction rates observed in the clinical trials of a drug cannot be directly compared to rates in the clinical trials of another drug and may not reflect the rates observed in clinical practice.
The most common adverse reactions (≥3%) reported in clinical trials when all three components of this therapy were given concomitantly for 14 days are listed in Table 8.

Table 8: Adverse Reactions Most Frequently Reported in Clinical Trials (≥3%)
Adverse Reaction | Triple Therapy n = 138 (%)
Diarrhea | 7.0
Headache | 6.0
Taste Perversion | 5.0

The additional adverse reactions which were reported as possibly or probably related to treatment (less than 3%) in clinical trials when all three components of this therapy were given concomitantly are listed below and divided by body system:
Body as a Whole - abdominal pain
Digestive System - dark stools, dry mouth/thirst, glossitis, rectal itching, nausea, oral moniliasis, stomatitis, tongue discoloration, tongue disorder, vomiting
Musculoskeletal System - myalgia
Nervous System - confusion, dizziness
Respiratory System - respiratory disorders
Skin and Appendages - skin reactions
Urogenital System - vaginitis, vaginal moniliasis
There were no statistically significant differences in the frequency of reported adverse events between the 10 and 14 day triple therapy regimens.
Lansoprazole Delayed-Release Capsules
The following adverse reactions from the labeling for lansoprazole delayed-release capsules are provided for information:
Worldwide, over 10,000 patients have been treated with lansoprazole delayed-release capsules in Phase 2 or Phase 3 clinical trials involving various dosages and durations of treatment. In general, lansoprazole delayed-release capsules treatment has been well-tolerated in both short-term and long-term trials.
Incidence in Clinical Trials
The following adverse events were reported by the treating physician to have a possible or probable relationship to drug in 1% or more of lansoprazole delayed-release capsules-treated patients and occurred at a greater rate in lansoprazole delayed-release capsules-treated patients than placebo-treated patients:

Table 9: Incidence of Possibly or Probably Treatment-Related Adverse Reactions in Short-Term, Placebo-Controlled Lansoprazole Delayed-Release Capsules Studies
Body System/Adverse Event | Lansoprazole Delayed-Release Capsules (N=2768) % | Placebo (N=1023)%
Body as a Whole
Abdominal Pain | 2.1 | 1.2
Digestive System
Constipation | 1.0 | 0.4
Diarrhea | 3.8 | 2.3
Nausea | 1.3 | 1.2

Headache was also seen at greater than 1% incidence but was more common on placebo. The incidence of diarrhea was similar between patients who received placebo and patients who received 30 mg of lansoprazole delayed-release capsules, but higher in the patients who received 60 mg of lansoprazole delayed-release capsules (2.9%, 4.2%, and 7.4%, respectively).
The most commonly reported possibly or probably treatment-related adverse event during maintenance therapy was diarrhea.
Additional adverse experiences occurring in less than 1% of patients or subjects who received lansoprazole delayed-release capsules in domestic trials are shown below:
Body as a Whole – abdomen enlarged, allergic reaction, asthenia, back pain, candidiasis, carcinoma, chest pain (not otherwise specified), chills, edema, fever, flu syndrome, halitosis, infection (not otherwise specified), malaise, neck pain, neck rigidity, pain, pelvic pain
Cardiovascular System – angina, arrhythmia, bradycardia, cerebrovascular accident/cerebral infarction, hypertension/hypotension, migraine, myocardial infarction, palpitations, shock (circulatory failure), syncope, tachycardia, vasodilation
Digestive System – abnormal stools, anorexia, bezoar, cardiospasm, cholelithiasis, colitis, dry mouth, dyspepsia, dysphagia, enteritis, eructation, esophageal stenosis, esophageal ulcer, esophagitis, fecal discoloration, flatulence, gastric nodules/fundic gland polyps, gastritis, gastroenteritis, gastrointestinal anomaly, gastrointestinal disorder, gastrointestinal hemorrhage, glossitis, gum hemorrhage, hematemesis, increased appetite, increased salivation, melena, mouth ulceration, nausea and vomiting, nausea and vomiting and diarrhea, gastrointestinal moniliasis, rectal disorder, rectal hemorrhage, stomatitis, tenesmus, thirst, tongue disorder, ulcerative colitis, ulcerative stomatitis
Endocrine System – diabetes mellitus, goiter, hypothyroidism
Hemic and Lymphatic System – anemia, hemolysis, lymphadenopathy
Metabolism and Nutritional Disorders – avitaminosis, gout, dehydration, hyperglycemia/hypoglycemia, peripheral edema, weight gain/loss
Musculoskeletal System – arthralgia, arthritis, bone disorder, joint disorder, leg cramps, musculoskeletal pain, myalgia, myasthenia, ptosis, synovitis
Nervous System – abnormal dreams, agitation, amnesia, anxiety, apathy, confusion, convulsion, dementia, depersonalization, depression, diplopia, dizziness, emotional lability, hallucinations, hemiplegia, hostility aggravated, hyperkinesia, hypertonia, hypesthesia, insomnia, libido decreased/increased, nervousness, neurosis, paresthesia, sleep disorder, somnolence, thinking abnormality, tremor, vertigo
Respiratory System – asthma, bronchitis, cough increased, dyspnea, epistaxis, hemoptysis, hiccup, laryngeal neoplasia, lung fibrosis, pharyngitis, pleural disorder, pneumonia, respiratory disorder, upper respiratory inflammation/infection, rhinitis, sinusitis, stridor
Skin and Appendages – acne, alopecia, contact dermatitis, dry skin, fixed eruption, hair disorder, maculopapular rash, nail disorder, pruritus, rash, skin carcinoma, skin disorder, sweating, urticaria
Special Senses – abnormal vision, amblyopia, blepharitis, blurred vision, cataract, conjunctivitis, deafness, dry eyes, ear/eye disorder, eye pain, glaucoma, otitis media, parosmia, photophobia, retinal degeneration/disorder, taste loss, taste perversion, tinnitus, visual field defect
Urogenital System – abnormal menses, breast enlargement, breast pain, breast tenderness, dysmenorrhea, dysuria, gynecomastia, impotence, kidney calculus, kidney pain, leukorrhea, menorrhagia, menstrual disorder, penis disorder, polyuria, testis disorder, urethral pain, urinary frequency, urinary retention, urinary tract infection, urinary urgency, urination impaired, vaginitis
Postmarketing
Additional adverse experiences have been reported since lansoprazole delayed-release capsules has been marketed. The majority of these cases are foreign-sourced and a relationship to lansoprazole delayed-release capsules has not been established. Because these events were reported voluntarily from a population of unknown size, estimates of frequency cannot be made. These events are listed below by COSTART body system:
Body as a Whole – anaphylactic/anaphylactoid reactions, systemic lupus erythematosus
Digestive System – hepatotoxicity, pancreatitis, vomiting
Hemic and Lymphatic System – agranulocytosis, aplastic anemia, hemolytic anemia, leukopenia, neutropenia, pancytopenia, thrombocytopenia, and thrombotic thrombocytopenic purpura
Infections and infestations – Clostridium difficile – associated diarrhea
Metabolism and Nutritional Disorders – hypomagnesemia, hyponatremia.
Musculoskeletal System – bone fracture, myositis
Skin and Appendages – severe dermatologic reactions including erythema multiforme, SJS, TEN (some fatal), DRESS, AGEP cutaneous lupus erythematosus
Special Senses – speech disorder
Urogenital System – interstitial nephritis, urinary retention, erectile dysfunction
Amoxicillin
The following adverse reactions from the labeling for amoxicillin are provided for information:
The most common adverse reactions (>1%) observed in clinical trials of amoxicillin capsules were diarrhea, rash, vomiting and nausea.
The most frequently reported adverse events for patients who received triple therapy (amoxicillin/clarithromycin/lansoprazole) were diarrhea (7%), headache (6%), and taste perversion (5%).
Infections and Infestations – Mucocutaneous candidiasis
Gastrointestinal - Drug-induced enterocolitis syndrome (DIES), black hairy tongue, and hemorrhagic/pseudomembranous colitis.
Onset of pseudomembranous colitis symptoms may occur during or after antibiotic treatment (see WARNINGS).
Hypersensitivity Reactions – Anaphylaxis (see WARNINGS), serum sickness-like reactions, erythematous maculopapular rashes, erythema multiforme, Stevens-Johnson Syndrome, exfoliative dermatitis, toxic epidermal necrolysis, acute generalized exanthematous pustulosis, linear IgA bullous dermatosis, hypersensitivity vasculitis and urticaria have been reported.
Liver – A moderate rise in AST and/or ALT has been noted, but the significance of this finding is unknown. Hepatic dysfunction including cholestatic jaundice, hepatic cholestasis and acute cytolytic hepatitis have been reported.
Renal – Crystalluria has also been reported (see OVERDOSAGE).
Hemic and Lymphatic Systems – Anemia, including hemolytic anemia, thrombocytopenia, thrombocytopenic purpura, eosinophilia, leukopenia and agranulocytosis have been reported. These reactions are usually reversible on discontinuation of therapy and are believed to be hypersensitivity phenomena.
Central Nervous System – Reversible hyperactivity, agitation, anxiety, insomnia, confusion, behavioral changes, and/or dizziness have been reported rarely.
Miscellaneous – Tooth discoloration (brown, yellow, or gray staining) has been rarely reported. Most reports occurred in pediatric patients. Discoloration was reduced or eliminated with brushing or dental cleaning in most cases.
Clarithromycin
The following adverse reactions from the labeling for clarithromycin are provided for information:
The most frequent and common adverse reactions related to clarithromycin therapy for both adult and pediatric populations are abdominal pain, diarrhea, nausea, vomiting, and dysgeusia. These adverse reactions are consistent with the known safety profile of macrolide antibiotics.
There was no significant difference in the incidence of these gastrointestinal adverse reactions during clinical trials between the patient population with or without preexisting mycobacterial infections.
Adverse Reactions Observed During Clinical Trials of Clarithromycin
The following adverse reactions were observed in clinical trials with clarithromycin at a rate greater than or equal to 1%:
Gastrointestinal Disorders – Diarrhea, vomiting, dyspepsia, nausea, abdominal pain
Hepatobiliary Disorders – Liver function test abnormal
Immune System Disorders – Anaphylactoid reaction
Infections and Infestations – Candidiasis
Nervous System Disorders – Dysgeusia, headache
Psychiatric Disorders – Insomnia
Skin and Subcutaneous Tissue Disorders – Rash
Other Adverse Reactions Observed During Clinical Trials of Clarithromycin
The following adverse reactions were observed in clinical trials with clarithromycin at a rate less than 1%:
Blood and Lymphatic System Disorders – Leukopenia, neutropenia, thrombocythemia, eosinophilia
Cardiac Disorders – Electrocardiogram QT prolonged, cardiac arrest, atrial fibrillation, extrasystoles, palpitations
Ear and Labyrinth Disorders – Vertigo, tinnitus, hearing impaired
Gastrointestinal Disorders – Stomatitis, glossitis, esophagitis, gastroesophageal reflux disease, gastritis, proctalgia, abdominal distention, constipation, dry mouth, eructation, flatulence
General Disorders and Administration Site Conditions – Malaise, pyrexia, asthma, chest pain, chills, fatigue
Hepatobiliary Disorders – Cholestasis, hepatitis
Immune System Disorders – Hypersensitivity
Infections and Infestations – Cellulitis, gastroenteritis, infection, vaginal infection
Investigations – Blood bilirubin increased, blood alkaline phosphatase increased, blood lactate dehydrogenase increased, albumin globulin ratio abnormal
Metabolism and Nutrition Disorders – Anorexia, decreased appetite
Musculoskeletal and Connective Tissue Disorders – Myalgia, muscle spasms, nuchal rigidity
Nervous System Disorders – Dizziness, tremor, loss of consciousness, dyskinesia, somnolence
Psychiatric Disorders – Anxiety, nervousness
Renal and Urinary Disorders – Blood creatinine increased, blood urea increased
Respiratory, Thoracic and Mediastinal Disorders – Asthma, epistaxis, pulmonary embolism
Skin and Subcutaneous Tissue Disorders – Urticaria, dermatitis bollus, pruritus, hyperhidrosis, rash maculopapular
The following adverse reactions have been identified during post approval use of clarithromycin. Because these reactions are reported voluntarily from a population of uncertain size, it is not always possible to reliably estimate their frequency or establish a causal relationship to drug exposure.
Blood and Lymphatic System Disorders – Thrombocytopenia, agranulocytosis
Cardiac Disorders – Torsades de pointes, ventricular tachycardia, ventricular arrhythmia
Ear and Labyrinth Disorders – Deafness was reported chiefly in elderly women and was usually reversible.
Gastrointestinal Disorders – Pancreatitis acute, tongue discoloration, tooth discoloration was reported and was usually reversible with professional cleaning upon discontinuation of the drug.
Hepatobiliary Disorders – Hepatic failure, jaundice hepatocellular. Adverse reactions related to hepatic dysfunction have been reported with clarithromycin (see WARNINGS, Hepatotoxicity)
Immune System Disorders – Anaphylactic reaction
Infections and Infestations – Pseudomembranous colitis
Investigations – Prothrombin time prolonged, white blood cell count decreased, international normalized ratio increased. Abnormal urine color has been reported, associated with hepatic failure.
Metabolism and Nutrition Disorders – Hypoglycemia has been reported in patients taking oral hypoglycemic agents or insulin.
Musculoskeletal and Connective Tissue Disorders – Myopathy, rhabdomyolysis was reported and in some of the reports, clarithromycin was administered concomitantly with statins, fibrates, colchicines or allopurinol (see CONTRAINDICATIONS and WARNINGS).
Nervous System Disorders – Convulsion, ageusia, parosmia, anosmia, paresthesia
Psychiatric Disorders – Psychotic disorder, confusional state, depersonalization, depression, disorientation, manic behavior, hallucination, abnormal behavior, abnormal dreams. These disorders usually resolve upon discontinuation of the drug.
There are no data on the effect of clarithromycin on the ability to drive or use machines. The potential for dizziness, vertigo, confusion and disorientation, which may occur with the medication, should be taken into account before patients drive or use machines.
Renal and Urinary Disorders – Nephritis interstitial, renal failure
Skin and Subcutaneous Tissue Disorders – Stevens-Johnson Syndrome, toxic epidermal necrolysis, drug rash with eosinophilia and systemic symptoms (DRESS), Henoch-Schonlein purpura, acne
Vascular Disorders – Hemorrhage
There have been reports of colchicine toxicity with concomitant use of clarithromycin and colchicine, especially in the elderly, some of which occurred in patients with renal insufficiency. Deaths have been reported in some such patients (see WARNINGS and PRECAUTIONS).
Laboratory Values
Lansoprazole Delayed-Release Capsules
The following changes in laboratory parameters in patients who received lansoprazole delayed-release capsules were reported as adverse reactions:
Abnormal liver function tests, increased SGOT (AST), increased SGPT (ALT), increased creatinine, increased alkaline phosphatase, increased globulins, increased GGTP, increased/decreased/abnormal WBC, abnormal AG ratio, abnormal RBC, bilirubinemia, blood potassium increased, blood urea increased, crystal urine present, eosinophilia, hemoglobin decreased, hyperlipemia, increased/decreased electrolytes, increased/decreased cholesterol, increased glucocorticoids, increased LDH, increased/decreased/abnormal platelets, increased gastrin levels and positive fecal occult blood. Urine abnormalities such as albuminuria, glycosuria, and hematuria were also reported.
In the placebo-controlled studies, when SGOT (AST) and SGPT (ALT) were evaluated, 0.4% (4/978) and 0.4% (11/2677) patients, who received placebo and lansoprazole delayed-release capsules, respectively, had enzyme elevations greater than three times the upper limit of normal range at the final treatment visit. None of these patients who received lansoprazole delayed-release capsules reported jaundice at any time during the study.

OVERDOSAGE

In case of an overdose, patients should contact a physician, poison control center, or emergency room. There is neither a pharmacologic basis nor data suggesting an increased toxicity of the combination compared to individual components.
In the event of over-exposure, treatment should be symptomatic and supportive.
If over-exposure occurs, call your poison control center at 1-800-222-1222 for current information on the management of poisoning or over-exposure.
Amoxicillin
In case of amoxicillin overdosage, discontinue medication, treat symptomatically and institute supportive measures as needed. If the overdosage is very recent and there is no contraindication, an attempt at emesis or other means of removal of drug from the stomach may be performed. A prospective study of 51 pediatric patients at a poison-control center suggested that overdosages of less than 250 mg/kg of amoxicillin are not associated with significant clinical symptoms and do not require gastric emptying.^2
Interstitial nephritis resulting in oliguric renal failure has been reported in a small number of patients after overdosage with amoxicillin.
Crystalluria, in some cases leading to renal failure, has also been reported after amoxicillin overdosage in adult and pediatric patients. In case of overdosage, adequate fluid intake and diuresis should be maintained to reduce the risk of amoxicillin crystalluria. Renal impairment appears to be reversible with cessation of drug administration. High blood levels may occur more readily in patients with impaired renal function because of decreased renal clearance of amoxicillin. Amoxicillin can be removed from circulation by hemodialysis.
Clarithromycin
Overdosage of clarithromycin can cause gastrointestinal symptoms such as abdominal pain, vomiting, nausea, and diarrhea.
Adverse reactions accompanying overdosage should be treated by the prompt elimination of unabsorbed drug and supportive measures. As with other macrolides, clarithromycin serum concentrations are not expected to be appreciably affected by hemodialysis or peritoneal dialysis.
Lansoprazole Delayed-Release Capsules
Lansoprazole is not removed from the circulation by hemodialysis. In one reported overdose, a patient consumed 600 mg of lansoprazole delayed-release capsules with no adverse reaction. Oral lansoprazole delayed-release capsules doses up to 5000 mg/kg in rats (approximately 650 times the recommended human dose of 60 mg/day based on BSA) and in mice (about 338 times the recommended human dose of 60 mg/day based on BSA) did not produce deaths or any clinical signs.

DOSAGE AND ADMINISTRATION

H. pylori Eradication to Reduce the Risk of Duodenal Ulcer Recurrence
The recommended adult oral dose is 30 mg lansoprazole delayed-release capsules, 1 g amoxicillin, and 500 mg clarithromycin administered together twice daily (morning and evening) for 10 or 14 days (see INDICATIONS AND USAGE).
Lansoprazole delayed-release capsules, 30 mg, amoxicillin capsules, 500 mg, and clarithromycin tablets, 500 mg are not recommended in patients with creatinine clearance less than 30 mL/min.

HOW SUPPLIED

Lansoprazole delayed-release capsules USP, 30 mg, amoxicillin capsules USP, 500 mg, and clarithromycin tablets USP, 500 mg are supplied in boxes of 14 daily administration cards, each card containing:
Lansoprazole Delayed-Release Capsules USP
Two size '1' capsules with dark blue color body and pink color cap, printed NATCO on cap and 30 on body with white ink are filled with white to off white colored spherical shaped pellets.
Amoxicillin Capsules USP
Four blue/pink size "0EL" hard gelatin capsules filled with white to off white granular powder and imprinted with "A45" on pink body with black ink.
Clarithromycin Tablets USP
Two light yellow colored, oval shaped, biconvex film-coated tablets, with 'D' debossed on one side and '63' on the other side.
NDC 57237-001-14 Carton containing 14 daily administration cards
NDC 57237-001-01 Daily administration card
Store between 20ºC to 25ºC (68ºF to 77ºF) [see USP Controlled Room Temperature]. Protect from light and moisture.

REFERENCES

1. CLSI. Methods for Antimicrobial Dilution and Disk Diffusion Susceptibility Testing of Infrequently Isolated or Fastidious Bacteria – 2nd edition. CLSI document M45-A2, 2010.
2. Swanson Biearman B, Dean BS, Lopez G, Krenzelok EP. The effects of penicillin and cephalosporin ingestions in children less than six years of age. Vet Hum Toxicol. 1988; 30:66-67.

Manufactured for:
Rising Pharma Holdings, Inc.
East Brunswick, NJ 08816

Lansoprazole Delayed-Release Capsules USP are
Manufactured by:
Natco Pharma Limited
Kothur-509 228, INDIA.

Amoxicillin Capsules USP are
Manufactured by:
Aurobindo Pharma Limited
Hyderabad-500 090, India

Clarithromycin Tablets USP are
Manufactured by:
Aurobindo Pharma Limited
Hyderabad-500 090, India

The brands listed are trademarks of their respective owners and are not trademarks of Aurobindo Pharma Limited.

Revised: 02/2025

PIR00114-06

PACKAGE LABEL-PRINCIPAL DISPLAY PANEL - 30 mg/500 mg/500 mg Carton Label

Rising NDC 57237-001-14
triple therapy
Lansoprazole Delayed-Release
Capsules USP, 30 mg
Amoxicillin Capsules USP, 500 mg
Clarithromycin Tablets USP, 500 mg

EACH DAILY PATIENT CARD CONTAINS:
2 Lansoprazole Delayed-Release Capsules USP, 30 mg;
4 Amoxicillin Capsules USP, 500 mg; and
2 Clarithromycin Tablets USP, 500 mg

14 DAILY PATIENT CARDS Rx only